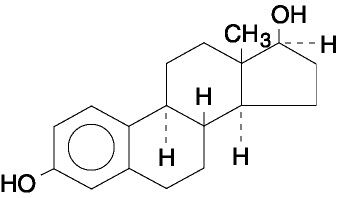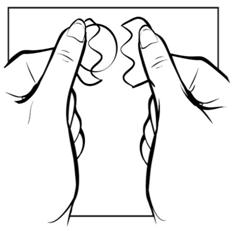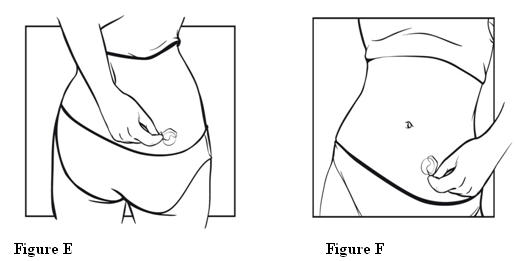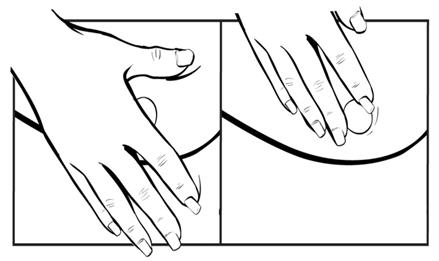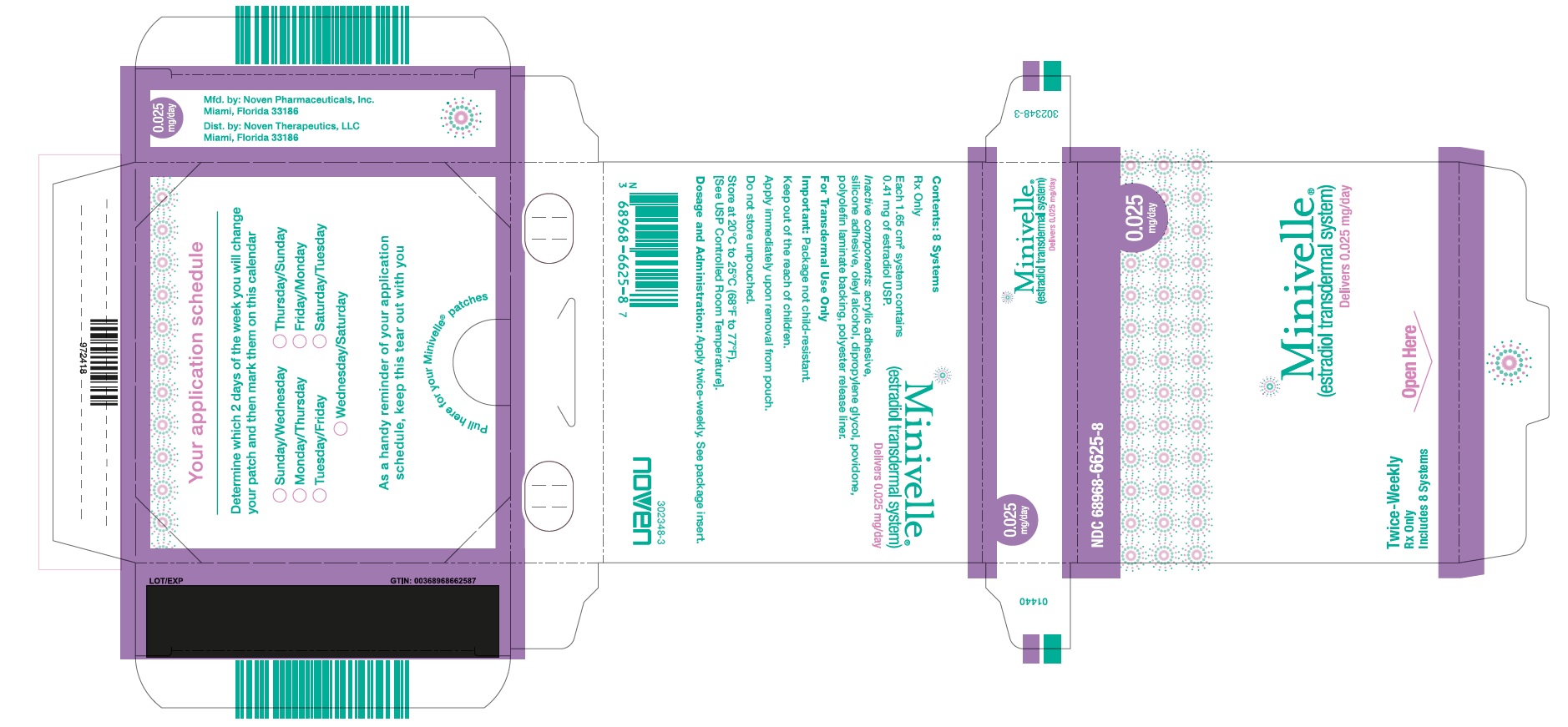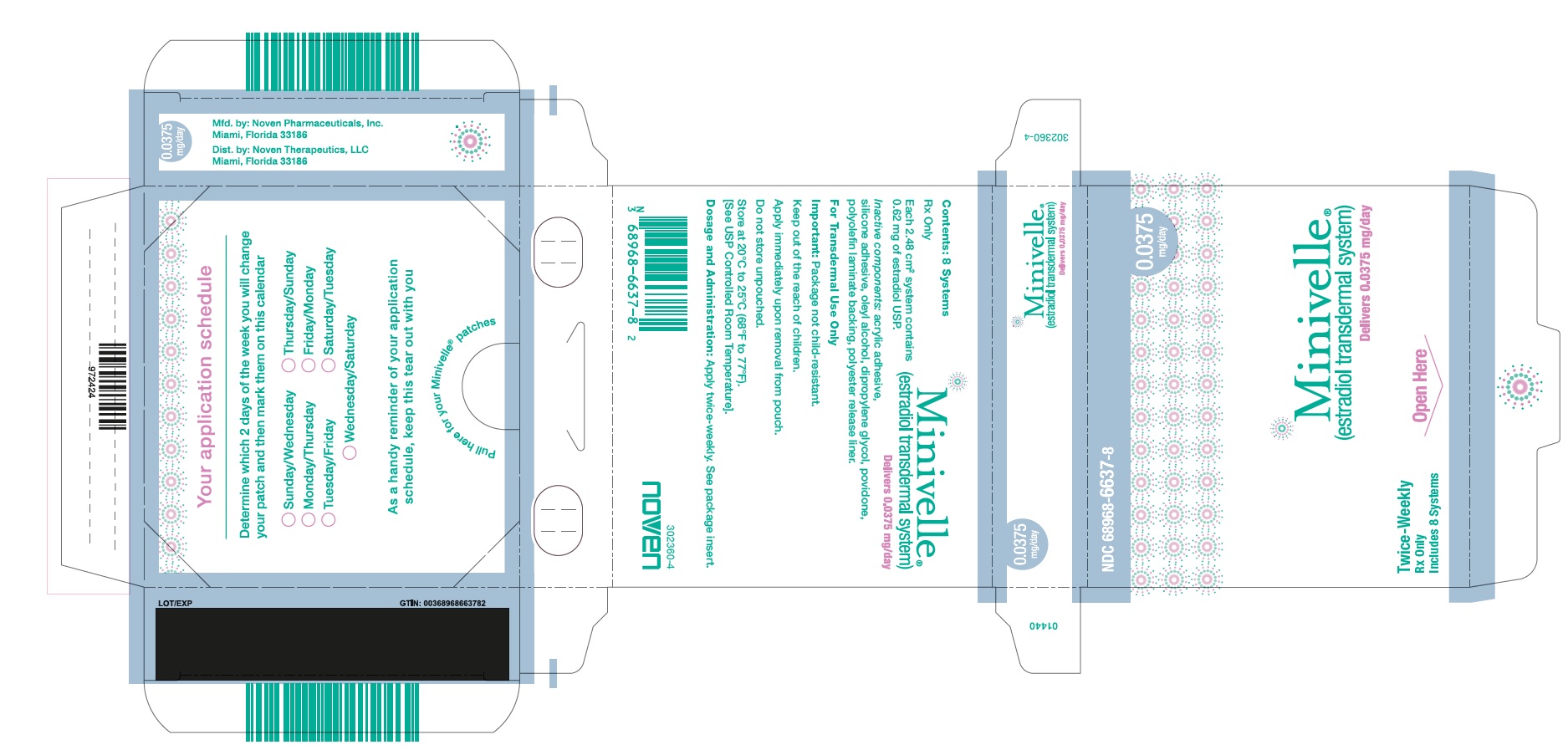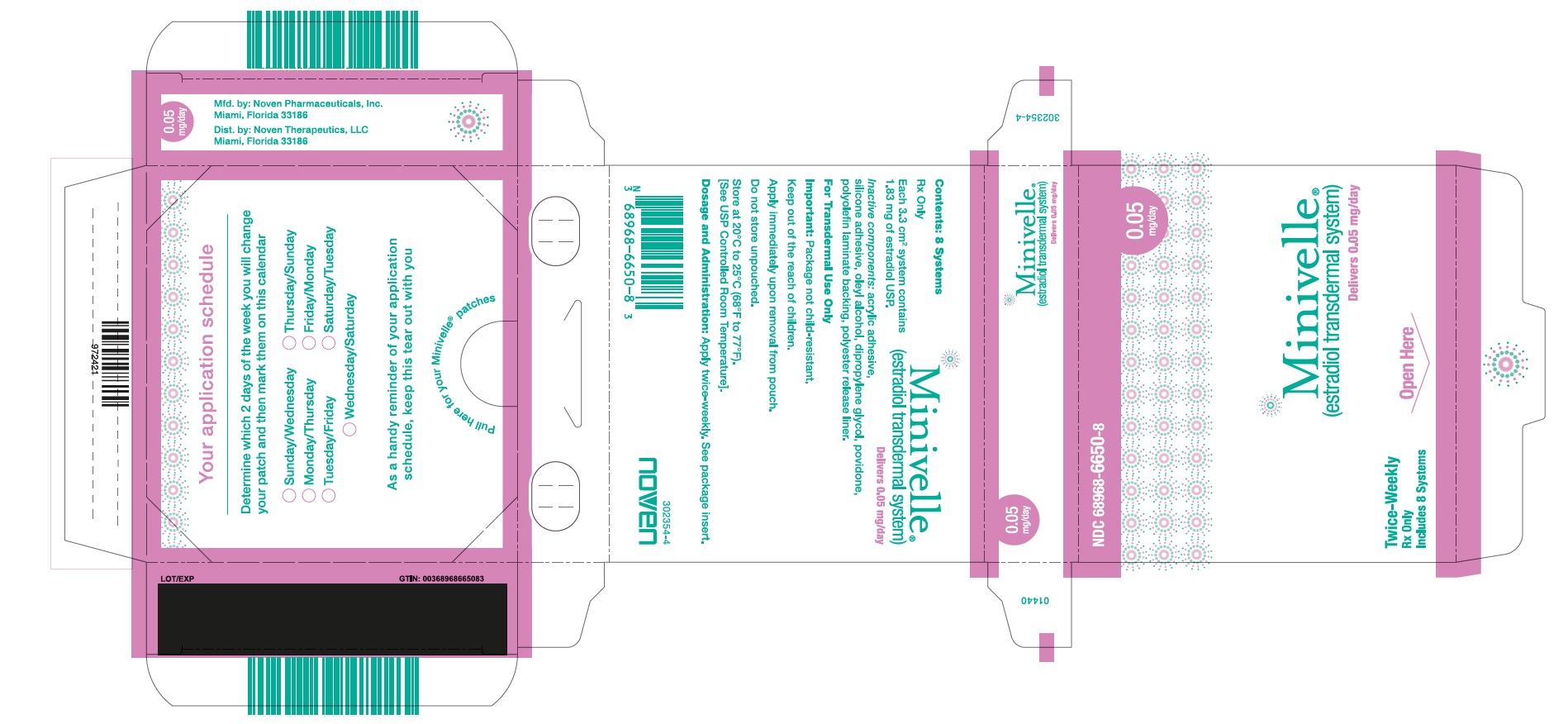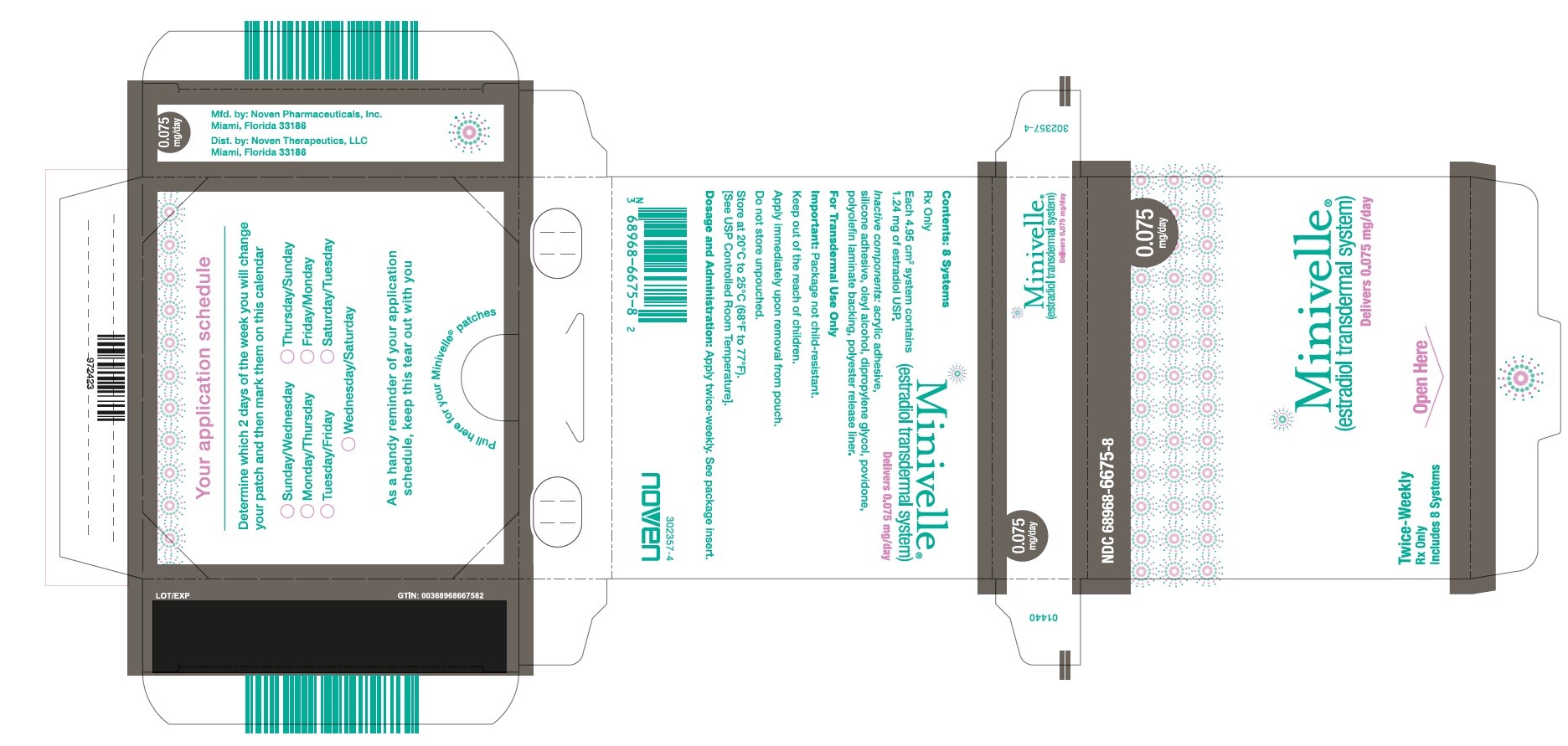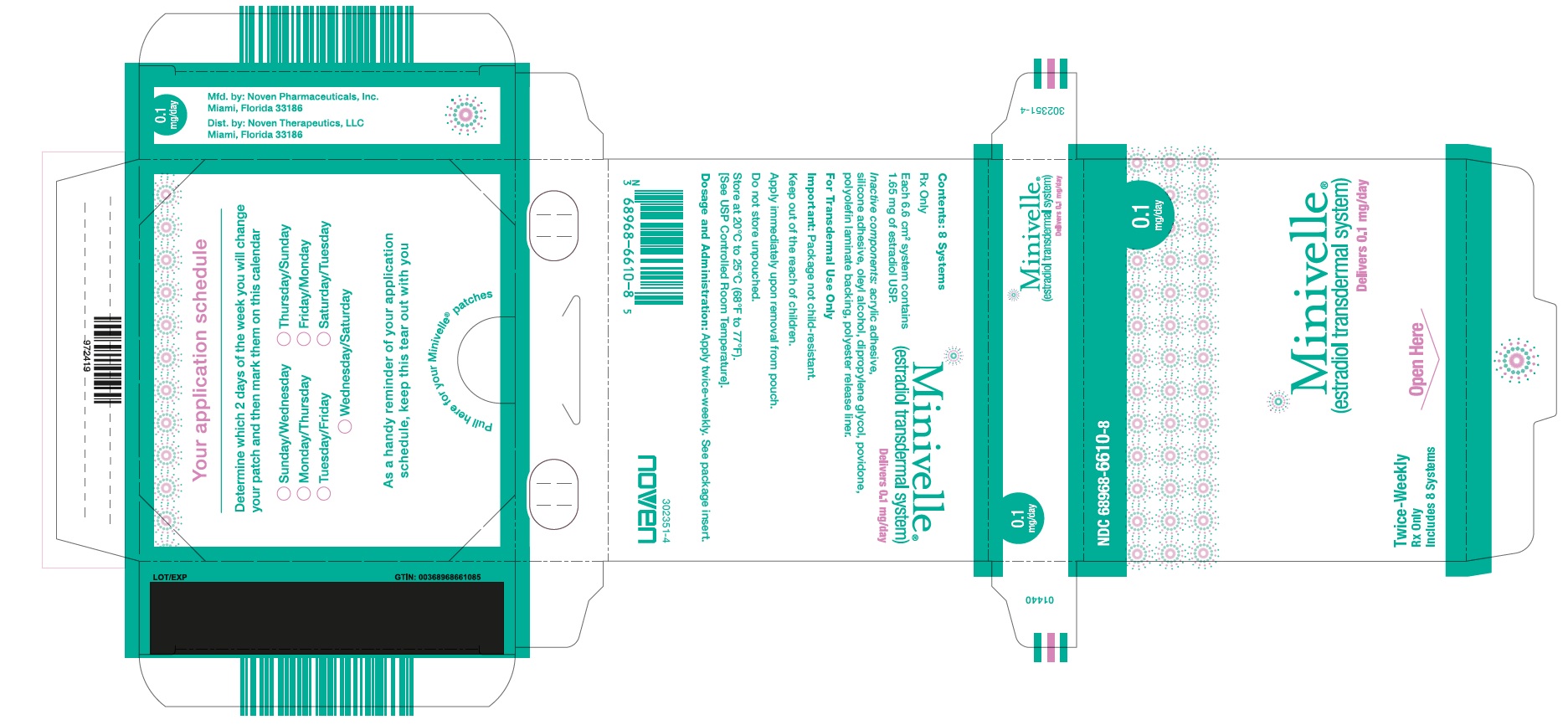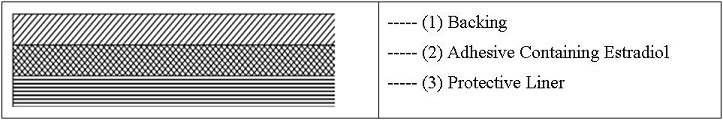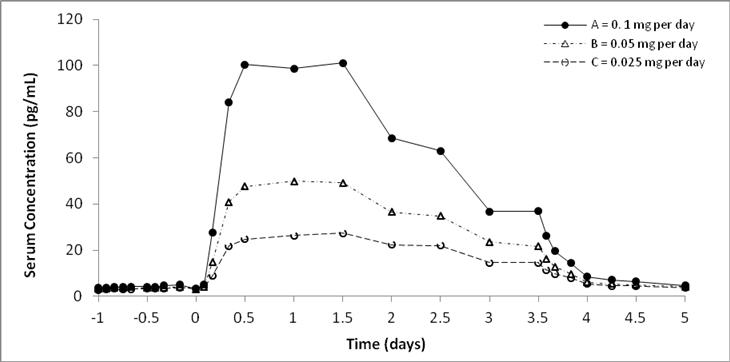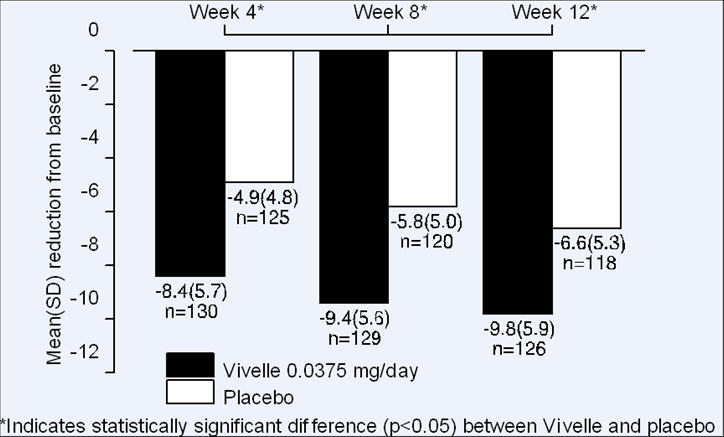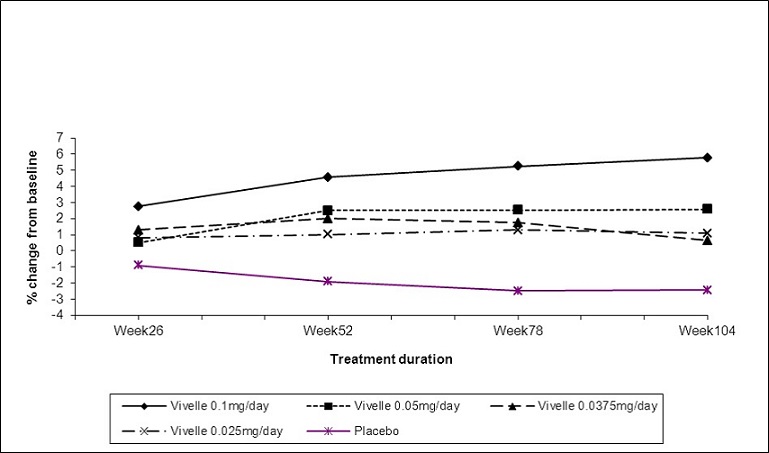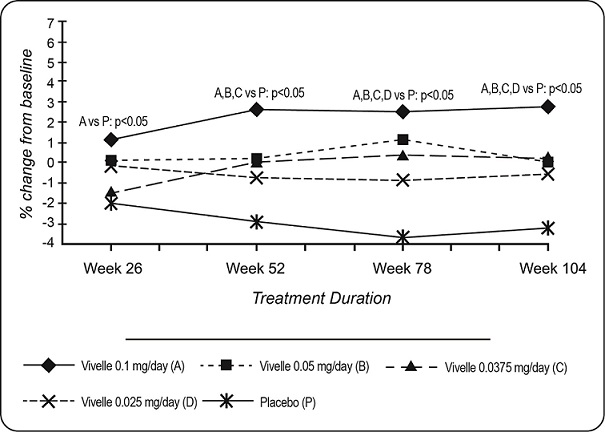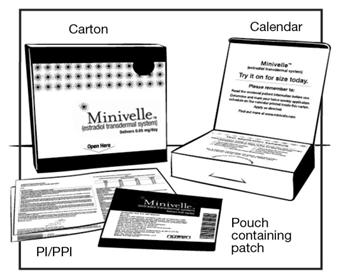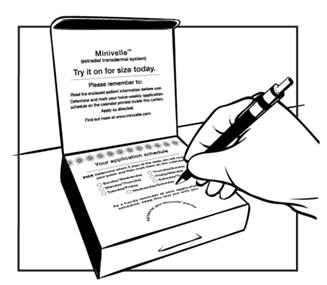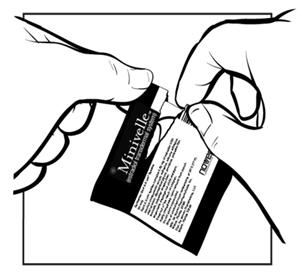 DRUG LABEL: Minivelle
NDC: 68968-6625 | Form: FILM, EXTENDED RELEASE
Manufacturer: Noven Therapeutics, LLC
Category: prescription | Type: HUMAN PRESCRIPTION DRUG LABEL
Date: 20240222

ACTIVE INGREDIENTS: ESTRADIOL 0.025 mg/1 d
INACTIVE INGREDIENTS: DIPROPYLENE GLYCOL; OLEYL ALCOHOL; POVIDONE K30

HIGHLIGHTS OF PRESCRIBING INFORMATION

These highlights do not include all the information needed to use MINIVELLE safely and effectively. See full prescribing information for MINIVELLE.
MINIVELLE® (estradiol transdermal system)
Initial U.S. Approval: 1975

WARNING: ENDOMETRIAL CANCER, CARDIOVASCULAR DISORDERS, PROBABLE DEMENTIA, and BREAST CANCER

WARNING: ENDOMETRIAL CANCER, CARDIOVASCULAR DISORDERS, PROBABLE DEMENTIA, and BREST CANCER
See full prescribing information for complete boxed warning.

Estrogen-Alone Therapy

- There is an increased risk of endometrial cancer in a woman with a uterus who uses unopposed estrogens (5.2)
- The Women’s Health Initiative (WHI) estrogen-alone substudy reported increased risks of stroke and deep vein thrombosis (DVT) (5.1)
- The WHI Memory Study (WHIMS) estrogen-alone ancillary study of WHI reported an increased risk of probable dementia in postmenopausal women 65 years of age and older (5.3)
- Do not use estrogen-alone therapy for the prevention of cardiovascular disease or dementia (5.1, 5.3)

Estrogen Plus Progestin Therapy

- The WHI estrogen plus progestin substudy reported increased risks of DVT, pulmonary embolism (PE), stroke, and myocardial infarction (MI) (5.1)
- The WHI estrogen plus progestin substudy reported increased risks of invasive breast cancer (5.2)
- The WHIMS estrogen plus progestin ancillary study of WHI reported an increased risk of probable dementia in postmenopausal women 65 years of age and older (5.3)
- Do not use estrogen plus progestogen therapy for the prevention of cardiovascular disease or dementia (5.1, 5.3)

RECENT MAJOR CHANGES

Warnings and Precautions, Malignant Neoplasms (5.2) | 02/2024

1 INDICATIONS AND USAGE

MINIVELLE® is an estrogen indicated for:

- Treatment of moderate to severe vasomotor symptoms due to menopause (1.1)
- Prevention of postmenopausal osteoporosis (1.2)

Limitations of Use

When prescribing solely for the treatment of postmenopausal osteoporosis, first consider the use of non-estrogen medications. Consider estrogen therapy only for women at significant risk of osteoporosis.

2 DOSAGE AND ADMINISTRATION

Start therapy with MINIVELLE® 0.0375 mg per day applied to the skin twice weekly for the treatment of moderate to severe vasomotor symptoms due to menopause. Dosage adjustment should be guided by the clinical response (2.1)

Start therapy with MINIVELLE 0.025 mg per day applied to the skin twice weekly for the prevention of postmenopausal osteoporosis. The dose may be adjusted as necessary (2.2)

Place MINIVELLE on a clean, dry area on the lower abdomen (below the umbilicus) or buttocks. Do not apply MINIVELLE to the breasts (2.3)

3 DOSAGE FORMS AND STRENGTHS

Transdermal system: 0.025 mg/day, 0.0375 mg/day, 0.05 mg/day, 0.075 mg/day, and 0.1 mg/day (3)

4 CONTRAINDICATIONS

- Undiagnosed abnormal genital bleeding (4, 5.2)
- Breast cancer or a history of breast cancer (4, 5.2)
- Estrogen-dependent neoplasia (4, 5.2)
- Active DVT, PE, or a history of these conditions (4, 5.1)
- Active arterial thromboembolic disease (for example, stroke or MI), or a history of these conditions (4, 5.1)
- Known anaphylactic reaction, angioedema, or hypersensitivity to MINIVELLE (4)
- Hepatic impairment or disease (4, 5.10)
- Protein C, protein S, or antithrombin deficiency, or other known thrombophilic disorders (4)

5 WARNINGS AND PRECAUTIONS

Estrogens increase the risk of gallbladder disease (5.4)

Discontinue estrogen if severe hypercalcemia, loss of vision, severe hypertriglyceridemia or cholestatic jaundice occurs (5.5, 5.6, 5.9, 5.10)

Monitor thyroid function in women on thyroid replacement therapy (5.11, 5.18)

6 ADVERSE REACTIONS

The most common adverse reactions (greater than or equal to 5 percent) with MINIVELLE are: headache, breast tenderness, back pain, pain in limb, nasopharyngitis, dyspepsia, nausea, sinusitis, and intermenstrual bleeding. (6.1)

To report SUSPECTED ADVERSE REACTIONS, contact Noven at 1-800-455-8070 or FDA at 1-800-FDA-1088 or www.fda.gov/medwatch.

7 DRUG INTERACTIONS

Inducers and/or inhibitors of CYP3A4 may affect estrogen drug metabolism and decrease or increase the estrogen plasma concentration. (7)

FULL PRESCRIBING INFORMATION

WARNING: ENDOMETRIAL CANCER, CARDIOVASCULAR DISORDERS, PROBABLE DEMENTIA, and BREAST CANCER

Estrogen-Alone Therapy

Endometrial Cancer

There is an increased risk of endometrial cancer in a woman with a uterus who uses unopposed estrogens. Adding a progestogen to estrogen therapy has been shown to reduce the risk of endometrial hyperplasia, which may be a precursor to endometrial cancer. Perform adequate diagnostic measures, including directed or random endometrial sampling when indicated, to rule out malignancy in postmenopausal women with undiagnosed persistent or recurring abnormal genital bleeding [see Warnings and Precautions (5.2)].

Cardiovascular Disorders and Probable Dementia

The Women’s Health Initiative (WHI) estrogen-alone substudy reported increased risks of stroke and deep vein thrombosis (DVT) in postmenopausal women (50 to 79 years of age) during 7.1 years of treatment with daily oral conjugated estrogens (CE) [0.625 mg]-alone, relative to placebo [see Warnings and Precautions (5.1), and Clinical Studies (14.3)].

The WHI Memory Study (WHIMS) estrogen-alone ancillary study of WHI reported an increased risk of developing probable dementia in postmenopausal women 65 years of age and older during 5.2 years of treatment with daily CE (0.625 mg)-alone, relative to placebo. It is unknown whether this finding applies to younger postmenopausal women [see Warnings and Precautions (5.3), Use in Specific Populations (8.5), and Clinical Studies (14.4)].

Do not use estrogen-alone therapy for the prevention of cardiovascular disease or dementia [see Warnings and Precautions (5.1, 5.3), and Clinical Studies (14.3, 14.4)].

Only daily oral 0.625 mg CE was studied in the estrogen-alone substudy of the WHI. Therefore, the relevance of the WHI findings regarding adverse cardiovascular events and dementia to lower CE doses, other route of administration, or other estrogen-alone products is not known. Without such data, it is not possible to definitively exclude these risks or determine the extent of these risks for other products. Discuss with your patient the benefits and risks of estrogen-alone therapy, taking into account her individual risk profile.

Prescribe estrogens with or without progestogens at the lowest effective doses and for the shortest duration consistent with treatment goals and risks for the individual woman.

Estrogen Plus Progestin Therapy

Cardiovascular Disorders and Probable Dementia

The WHI estrogen plus progestin substudy reported increased risks of DVT, pulmonary embolism (PE), stroke and myocardial infarction (MI) in postmenopausal women (50 to 79 years of age) during 5.6 years of treatment with daily oral CE (0.625 mg) combined with medroxyprogesterone acetate (MPA) [2.5 mg], relative to placebo [see Warnings and Precautions (5.1), and Clinical Studies (14.3)].

The WHIMS estrogen plus progestin ancillary study of the WHI, reported an increased risk of developing probable dementia in postmenopausal women 65 years of age and older during 4 years of treatment with daily CE (0.625 mg) combined with MPA (2.5 mg), relative to placebo. It is unknown whether this finding applies to younger postmenopausal women [see Warnings and Precautions (5.3), Use in Specific Populations (8.5), and Clinical Studies (14.4)].

Do not use estrogen plus progestogen therapy for the prevention of cardiovascular disease or dementia [see Warnings and Precautions (5.1, 5.3), and Clinical Studies (14.3, 14.4)].

Breast Cancer

The WHI estrogen plus progestin substudy also demonstrated an increased risk of invasive breast cancer [see Warnings and Precautions (5.2), and Clinical Studies (14.3)].

Only daily oral 0.625 mg CE and 2.5 mg MPA were studied in the estrogen plus progestin substudy of the WHI. Therefore, the relevance of the WHI findings regarding adverse cardiovascular events, dementia and breast cancer to lower CE plus other MPA doses, other routes of administration, or other estrogen plus progestogen products is not known. Without such data, it is not possible to definitively exclude these risks or determine the extent of these risks for other products. Discuss with your patient the benefits and risks of estrogen plus progestogen therapy, taking into account her individual risk profile.

Prescribe estrogens with or without progestogens at the lowest effective doses and for the shortest duration consistent with treatment goals and risks for the individual woman.

1 INDICATIONS AND USAGE

MINIVELLE is indicated for:

1.2 Prevention of Postmenopausal Osteoporosis

Limitation of Use

When prescribing solely for the prevention of postmenopausal osteoporosis, first consider the use of non-estrogen medications. Consider estrogen therapy only for women at significant risk of osteoporosis.

2 DOSAGE AND ADMINISTRATION

Generally, when estrogen is prescribed for a postmenopausal woman with a uterus, consider addition of a progestogen to reduce the risk of endometrial cancer. Generally, a woman without a uterus, does not need to use a progestogen in addition to her estrogen therapy. In some cases, however, hysterectomized women who have a history of endometriosis may need a progestogen [see Warnings and Precautions (5.2, 5.14)].

Use estrogen-alone, or in combination with a progestogen, at the lowest effective dose and for the shortest duration consistent with treatment goals and risks for the individual woman. Reevaluate postmenopausal women periodically as clinically appropriate to determine if treatment is still necessary.

2.1 Treatment of Moderate to Severe Vasomotor Symptoms due to Menopause

Start therapy with MINIVELLE 0.0375 mg per day applied to the skin twice weekly. Make dosage adjustments based on clinical response. Attempt to taper or discontinue MINIVELLE at 3 to 6 month intervals.

2.3 Application Instructions

Place the adhesive side of MINIVELLE on a clean, dry area on the lower abdomen (below the umbilicus) or buttocks. Do not apply MINIVELLE to the breasts.

Replace MINIVELLE twice weekly (every 3-4 days).

Rotate the sites of application, with an interval of at least 1 week allowed between applications to a particular site.

Select an area for application that is not oily, damaged, or irritated. Avoid the waistline, since tight clothing may rub the system off. Apply the system immediately after opening the pouch and removing the protective liner. Press the system firmly in place with the palm of the hand for about 10 seconds, making sure there is good contact with the skin, especially around the edges. In the event that a system falls off, reapply the same system or apply a new system to another location. In either case, continue the original treatment schedule. If a woman has forgotten to apply MINIVELLE, have her apply a new system as soon as possible. Apply the new system on the original treatment schedule. The interruption of treatment in women taking MINIVELLE might increase the likelihood of breakthrough bleeding, spotting and recurrence of symptoms.

3 DOSAGE FORMS AND STRENGTHS

Transdermal system: 0.025 mg/day, 0.0375 mg/day, 0.05 mg/day, 0.075 mg/day, and 0.1 mg/day.

4 CONTRAINDICATIONS

MINIVELLE is contraindicated in women with any of the following conditions:

- Undiagnosed abnormal genital bleeding [see Warnings and Precautions (5.2)].
- Breast cancer or a history of breast cancer [see Warnings and Precautions (5.2)].
- Estrogen-dependent neoplasia [see Warnings and Precautions (5.2)].
- Active DVT, PE, or a history of these conditions [see Warnings and Precautions (5.1)].
- Active arterial thromboembolic disease (for example, stroke or MI), or a history of these conditions [see Warnings and Precautions (5.1)].
- Known anaphylactic reaction, angioedema, or hypersensitivity to MINIVELLE
- Hepatic impairment or disease
- Protein C, protein S, or antithrombin deficiency, or other known thrombophilic disorders

5 WARNINGS AND PRECAUTIONS

5.1 Cardiovascular Disorder

Increased risks of stroke and DVT are reported with estrogen-alone therapy. Increased risks of PE, DVT, stroke and MI are reported with estrogen plus progestin therapy. Immediately discontinue estrogen with or without progestogen therapy if any of these occur or are suspected.

Manage appropriately any risk factors for arterial vascular disease (for example, hypertension, diabetes mellitus, tobacco use, hypercholesterolemia, and obesity) and/or venous thromboembolism (VTE) (for example, personal history or family history of VTE, obesity, and systemic lupus erythematosus).

Stroke

The WHI estrogen-alone substudy reported a statistically significant increased risk of stroke in women 50 to 79 years of age receiving daily CE (0.625 mg)-alone compared to women in the same age group receiving placebo (45 versus 33 strokes per 10,000 women-years, respectively). The increase in risk was demonstrated in year 1 and persisted [see Clinical Studies (14.3)]. Immediately discontinue estrogen-alone therapy if a stroke occurs or is suspected.

Subgroup analyses of women 50 to 59 years of age suggest no increased risk of stroke for those women receiving CE (0.625 mg)-alone versus those receiving placebo (18 versus 21 per 10,000 women-years).^1

The WHI estrogen plus progestin substudy reported a statistically significant increased risk of stroke in women 50 to 79 years of age receiving CE (0.625 mg) plus MPA (2.5 mg) compared to women in the same age group receiving placebo (33 versus 25 strokes per 10,000 women-years, respectively) [see Clinical Studies, (14.3)]. The increase in risk was demonstrated after the first year and persisted.^1 Immediately discontinue estrogen plus progestogen therapy if a stroke occurs or is suspected.

Subgroup analyses of women 50 to 59 years of age suggest no increased risk of stroke for those women receiving CE (0.625 mg)-alone versus those receiving placebo (18 versus 21 per 10,000 women-years).^1

The WHI estrogen plus progestin substudy reported a statistically significant increased risk of stroke in women 50 to 79 years of age receiving CE (0.625 mg) plus MPA (2.5 mg) compared to women in the same age group receiving placebo (33 versus 25 strokes per 10,000 women-years) [see Clinical Studies, (14.3)]. The increase in risk was demonstrated after the first year and persisted.^1 Immediately discontinue estrogen plus progestogen therapy if a stroke occurs or is suspected.

Coronary Heart Disease

The WHI estrogen-alone substudy reported no overall effect on coronary heart disease (CHD) events (defined as nonfatal MI, silent MI, or CHD death) in women receiving estrogen-alone compared to placebo^2 [see Clinical Studies (14.3)].

Subgroup analyses of women 50 to 59 years of age, who were less than 10 years since menopause, suggest a reduction (not statistically significant) of CHD events in those women receiving daily CE (0.625 mg)-alone compared to placebo (8 versus 16 per 10,000 women-years).^1

The WHI estrogen plus progestin substudy reported an increased risk (not statistically significant) of CHD events in women receiving daily CE (0.625 mg) plus MPA (2.5 mg) compared to women receiving placebo (41 versus 34 per 10,000 women years).^1 An increase in relative risk was demonstrated in year 1, and a trend toward decreasing relative risk was reported in years 2 through 5 [see Clinical Studies (14.3)].

In postmenopausal women with documented heart disease (n = 2,763, average 66.7 years of age), in a controlled clinical trial of secondary prevention of cardiovascular disease (Heart and Estrogen/Progestin Replacement Study; HERS), treatment with daily CE (0.625 mg) plus MPA (2.5 mg) demonstrated no cardiovascular benefit. During an average follow-up of 4.1 years, treatment with CE plus MPA did not reduce the overall rate of CHD events in postmenopausal women with established CHD. There were more CHD events in the CE plus MPA-treated group than in the placebo group in year 1, but not during the subsequent years. Two thousand, three hundred and twenty-one (2,321) women from the original HERS trial agreed to participate in an open-label extension of HERS, HERS II. Average follow-up in HERS II was an additional 2.7 years, for a total of 6.8 years overall. Rates of CHD events were comparable among women in the CE plus MPA group and the placebo group in the HERS, HERS II, and overall.

Venous Thromboembolism

In the WHI estrogen-alone substudy, the risk of VTE (DVT and PE), was increased for women receiving daily CE (0.625 mg)-alone compared to placebo (30 versus 22 per 10,000 women-years), although only the increased risk of DVT reached statistical significance (23 versus 15 per 10,000 women years). The increase in VTE risk was demonstrated during the first 2 years^3 [see Clinical Studies (14.3)]. Immediately discontinue estrogen-alone therapy if a VTE occurs or is suspected.

The WHI estrogen plus progestin substudy reported a statistically significant 2-fold greater rate of VTE in women receiving daily CE (0.625 mg) plus MPA (2.5 mg) compared to women receiving placebo (35 versus 17 per 10,000 women-years). Statistically significant increases in risk for both DVT (26 versus 13 per 10,000 women-years) and PE (18 versus 8 per 10,000 women-years) were also demonstrated. The increase in VTE risk was demonstrated during the first year and persisted^4 [see Clinical Studies (14.3)]. Immediately discontinue estrogen plus progestogen therapy if a VTE occurs or is suspected.

If feasible, discontinue estrogens at least 4 to 6 weeks before surgery of the type associated with an increased risk of thromboembolism, or during periods of prolonged immobilization.

5.2 Malignant Neoplasms

Endometrial Cancer

An increased risk of endometrial cancer has been reported with the use of unopposed estrogen therapy in women with a uterus. The reported endometrial cancer risk among unopposed estrogen users is about 2 to 12 times greater than in non-users and appears dependent on duration of treatment and on estrogen dose. Most studies show no significant increased risk associated with the use of estrogens for less than 1 year. The greatest risk appears to be associated with prolonged use, with increased risks of 15- to 24-fold for 5 to 10 years or more. This risk has been shown to persist for at least 8 to 15 years after estrogen therapy is discontinued.

Clinical surveillance of all women using estrogen-alone or estrogen plus progestogen therapy is important. Perform adequate diagnostic measures, including directed or random endometrial sampling when indicated, to rule out malignancy in postmenopausal women with undiagnosed persistent or recurring abnormal genital bleeding with unknown etiology.

There is no evidence that the use of natural estrogens results in a different endometrial risk profile than synthetic estrogens of equivalent estrogen dose. Adding a progestogen to estrogen therapy has been shown to reduce the risk of endometrial hyperplasia, which may be a precursor to endometrial cancer.

Breast Cancer

The WHI substudy of daily CE (0.625 mg)-alone provided information about breast cancer in estrogen-alone users. In the WHI estrogen-alone substudy, after an average follow-up of 7.1 years, daily CE-alone was not associated with an increased risk of invasive breast cancer (relative risk [RR] 0.80)^5 [see Clinical Studies (14.3)].

After a mean follow-up of 5.6 years, the WHI substudy of daily CE (0.625 mg) plus MPA (2.5 mg) reported an increased risk of invasive breast cancer in women who took daily CE plus MPA compared to placebo.

In this substudy, prior use of estrogen-alone or estrogen plus progestin therapy was reported by 26 percent of the women. The relative risk of invasive breast cancer was 1.24, and the absolute risk was 41 versus 33 cases per 10,000 women-years, for CE plus MPA compared with placebo. Among women who reported prior use of hormone therapy, the relative risk of invasive breast cancer was 1.86, and the absolute risk was 46 versus 25 cases per 10,000 women-years, for CE plus MPA compared with placebo.^6 Among women who reported no prior use of hormone therapy, the relative risk of invasive breast cancer was 1.09, and the absolute risk was 40 versus 36 cases per 10,000 women-years for CE plus MPA compared with placebo. In the same substudy, invasive breast cancers were larger, were more likely to be node positive, and were diagnosed at a more advanced stage in the CE (0.625 mg) plus MPA (2.5 mg) group compared with the placebo group. Metastatic disease was rare, with no apparent difference between the two groups. Other prognostic factors, such as histologic subtype, grade and hormone receptor status did not differ between the groups^6 [see Clinical Studies (14.3)].

Consistent with the WHI clinical trial, observational studies have also reported an increased risk of breast cancer with estrogen plus progestin therapy, and a smaller increase in the risk for breast cancer with estrogen-alone therapy, after several years of use. One large meta-analysis of prospective cohort studies reported increased risks that were dependent upon duration of use and could last up to >10 years after discontinuation of estrogen-alone therapy and estrogen plus progestin therapy. Extension of the WHI trials also demonstrated increased breast cancer risk associated with estrogen plus progestin therapy. Observational studies also suggest that the risk of breast cancer was greater, and became apparent earlier, with estrogen plus progestin therapy as compared to estrogen-alone therapy. These studies have not generally found significant variation in the risk of breast cancer among different estrogen plus progestin combinations, doses, or routes of administration.

The use of estrogen-alone and estrogen plus progestin has been reported to result in an increase in abnormal mammograms requiring further evaluation. All women should receive yearly breast examinations by a healthcare provider and perform monthly breast self-examinations. In addition, mammography examinations should be scheduled based on patient age, risk factors, and prior mammogram results.

Ovarian Cancer

The CE plus MPA substudy of WHI reported that estrogen plus progestin increased the risk of ovarian cancer. After an average follow-up of 5.6 years, the relative risk for CE plus MPA versus placebo was 1.58 (95 percent CI, 0.77-3.24), but it was not statistically significant. The absolute risk for CE plus MPA versus placebo was 4 versus 3 cases per 10,000 women-years.^7

A meta-analysis of 17 prospective and 35 retrospective epidemiology studies found that women who used hormonal therapy for menopausal symptoms had an increased risk for ovarian cancer. The primary analysis, using case-control comparisons, included 12,110 cancer cases from the 17 prospective studies. The relative risks associated with current use of hormonal therapy was 1.41 (95% confidence interval [CI] 1.32 to 1.50); there was no difference in the risk estimates by duration of the exposure (less than 5 years [median of 3 years] vs. greater than 5 years [median of 10 years] of use before the cancer diagnosis). The relative risk associated with combined current and recent use (discontinued use within 5 years before cancer diagnosis) was 1.37 (95% CI 1.27-1.48), and the elevated risk was significant for both estrogen-alone and estrogen plus progestin products. The exact duration of hormone therapy use associated with an increased risk of ovarian cancer, however, is unknown.

5.3 Probable Dementia

In the WHI Memory Study (WHIMS) estrogen-alone ancillary study, a population of 2,947 hysterectomized women 65 to 79 years of age was randomized to daily CE (0.625 mg)-alone or placebo.

After an average follow-up of 5.2 years, 28 women in the estrogen-alone group and 19 women in the placebo group were diagnosed with probable dementia. The relative risk of probable dementia for CE-alone versus placebo was 1.49 (95 percent CI, 0.83-2.66). The absolute risk of probable dementia for CE-alone versus placebo was 37 versus 25 cases per 10,000 women-years^8 [see Use in Specific Populations (8.5), and Clinical Studies (14.4)].

In the WHIMS estrogen plus progestin ancillary study of WHI, a population of 4,532 postmenopausal women 65 to 79 years of age was randomized to daily CE (0.625 mg) plus MPA (2.5 mg) or placebo.

After an average follow-up of 4 years, 40 women in the CE plus MPA group and 21 women in the placebo group were diagnosed with probable dementia. The relative risk of probable dementia for CE plus MPA versus placebo was 2.05 (95 percent CI, 1.21-3.48). The absolute risk of probable dementia for CE plus MPA versus placebo was 45 versus 22 cases per 10,000 women-years^8 [see Use in Specific Populations (8.5), and Clinical Studies (14.4)].

When data from the two populations in the WHIMS estrogen-alone and estrogen plus progestin ancillary studies were pooled as planned in the WHIMS protocol, the reported overall relative risk for probable dementia was 1.76 (95 percent CI, 1.19-2.60). Since both ancillary studies were conducted in women 65 to 79 years of age, it is unknown whether these findings apply to younger postmenopausal women^8 [see Use in Specific Populations (8.5), and Clinical Studies (14.4)].

5.4 Gallbladder Disease

A 2- to 4-fold increase in the risk of gallbladder disease requiring surgery in postmenopausal women receiving estrogens has been reported.

5.5 Hypercalcemia

Estrogen administration may lead to severe hypercalcemia in women with breast cancer and bone metastases. Discontinue estrogens, including MINIVELLE, if hypercalcemia occurs, and take appropriate measures to reduce the serum calcium level.

5.6 Visual Abnormalities

Retinal vascular thrombosis has been reported in women receiving estrogens. Discontinue MINIVELLE pending examination if there is sudden partial or complete loss of vision, or a sudden onset of proptosis, diplopia, or migraine. Permanently discontinue estrogens, including MINIVELLE, if examination reveals papilledema or retinal vascular lesions.

5.7 Addition of a Progestogen When a Woman Has Not Had a Hysterectomy

Studies of the addition of a progestogen for 10 or more days of a cycle of estrogen administration, or daily with estrogen in a continuous regimen, have reported a lowered incidence of endometrial hyperplasia than would be induced by estrogen treatment alone. Endometrial hyperplasia may be a precursor to endometrial cancer. There are, however, possible risks that may be associated with the use of progestogens with estrogens compared to estrogen-alone regimens. These include an increased risk of breast cancer.

5.8 Elevated Blood Pressure

In a small number of case reports, substantial increases in blood pressure have been attributed to idiosyncratic reactions to estrogens. In a large, randomized, placebo-controlled clinical trial, a generalized effect of estrogens on blood pressure was not seen.

5.9 Exacerbation of Hypertriglyceridemia

In women with pre-existing hypertriglyceridemia, estrogen therapy may be associated with elevations of plasma triglycerides leading to pancreatitis. Discontinue MINIVELLE if pancreatitis occurs.

5.10 Hepatic Impairment and/or Past History of Cholestatic Jaundice

Estrogens may be poorly metabolized in women with hepatic impairment. Exercise caution in any woman with a history of cholestatic jaundice associated with past estrogen use or with pregnancy. In the case of recurrence of cholestatic jaundice, discontinue MINIVELLE.

5.11 Exacerbation of Hypothyroidism

Estrogen administration leads to increased thyroid-binding globulin (TBG) levels. Women with normal thyroid function can compensate for the increased TBG by making more thyroid hormone, thus maintaining free T4 and T3 serum concentrations in the normal range. Women dependent on thyroid hormone replacement therapy who are also receiving estrogens may require increased doses of their thyroid replacement therapy. Monitor thyroid function in these women during treatment with MINIVELLE to maintain their free thyroid hormone levels in an acceptable range.

5.12 Fluid Retention

Estrogens may cause some degree of fluid retention. Monitor any woman with a condition(s) that might predispose her to fluid retention, such as cardiac or renal impairment. Discontinue estrogen-alone therapy, including MINIVELLE, with evidence of medically concerning fluid retention.

5.13 Hypocalcemia

Estrogen-induced hypocalcemia may occur in women with hypoparathyroidism. Consider whether the benefits of estrogen therapy, including MINIVELLE, outweigh the risks in such women.

5.14 Exacerbation of Endometriosis

A few cases of malignant transformation of residual endometrial implants have been reported in women treated post-hysterectomy with estrogen-alone therapy. Consider the addition of progestogen therapy for women known to have residual endometriosis post-hysterectomy.

5.15 Severe Anaphylactic/Anaphylactoid Reactions and Hereditary Angioedema

A few cases of anaphylactic/anaphylactoid reactions are reported in the postmarketing use of MINIVELLE. Involvement of skin (hives, pruritus, swollen lips-tongue-face) and either respiratory tract (respiratory compromise) or gastrointestinal tract (abdominal pain, vomiting) are noted.

Angioedema involving eye/eyelid, face, larynx, pharynx, tongue and extremity (hands, legs, ankles, and fingers) with or without urticaria requiring medical intervention are reported in the postmarketing use of MINIVELLE. Angioedema involving the tongue, glottis, or larynx, may result in airway obstruction. Do not give MINIVELLE to any woman who develops angioedema during treatment with Minivelle.

Exogenous estrogens may exacerbate symptoms of angioedema in women with hereditary angioedema. Consider whether the benefits of estrogen therapy outweigh the risks in such women.

5.16 Exacerbation of Other Conditions

Estrogen therapy, including MINIVELLE, may cause an exacerbation of asthma, diabetes mellitus, epilepsy, migraines, porphyria, systemic lupus erythematosus, and hepatic hemangiomas. Consider whether the benefits of estrogen therapy outweigh the risks in such women.

5.17 Laboratory Tests

Serum follicle stimulating hormone (FSH) and estradiol levels have not been shown to be useful in the management of postmenopausal women with moderate to severe vasomotor symptoms.

5.18 Drug-Laboratory Test Interactions

- Accelerated prothrombin time, partial thromboplastin time, and platelet aggregation time; increased platelet count; increased factors II, VII antigen, VIII antigen, VIII coagulant activity, IX, X, XII, VII-X complex, II-VII-X complex; and beta-thromboglobulin; decreased levels of antifactor Xa and antithrombin III; decreased antithrombin III activity; increased levels of fibrinogen and fibrinogen activity; increased plasminogen antigen and activity.
- Increased thyroid-binding globulin (TBG) leading to increased circulating total thyroid hormone levels, as measured by protein-bound iodine (PBI), T4 levels (by column or by radioimmunoassay) or T3 levels by radioimmunoassay. T3 resin uptake is decreased, reflecting the elevated TBG. Free T4 and free T3 concentrations are unaltered. Women on thyroid replacement therapy may require higher doses of thyroid hormone.
- Other binding proteins may be elevated in serum, for example, corticosteroid-binding globulin (CBG), sex hormone-binding globulin (SHBG), leading to increased total circulating corticosteroids and sex steroids, respectively. Free hormone concentrations, such as testosterone and estradiol, may be decreased. Other plasma proteins may be increased (angiotensinogen/renin substrate, alpha-1-antitrypsin, ceruloplasmin).
- Increased plasma high-density lipoprotein (HDL) and HDL2 cholesterol subfraction concentrations, reduced low-density lipoprotein (LDL) cholesterol concentration, and increased triglycerides levels.
- Impaired glucose tolerance.

6 ADVERSE REACTIONS

The following serious adverse reactions are discussed elsewhere in labeling:

- Cardiovascular Disorders [see Boxed Warning, Warning and Precaution, (5.1)]
- Malignant Neoplasms [see Boxed Warning, Warnings and Precautions (5.2)]

6.1 Clinical Trials Experience

Because clinical trials are conducted under widely varying conditions, adverse reaction rates observed in the clinical trials of a drug cannot be directly compared to rates in the clinical trials of another drug and may not reflect the rates observed in practice.

There were no clinical trials conducted with MINIVELLE. MINIVELLE is bioequivalent to Vivelle®. The following adverse reactions are reported with Vivelle therapy:

Table 1: Summary of Most Frequently Reported Adverse Reactions (Vivelle versus Placebo) Regardless of Relationship Reported at a Frequency ≥5 Percent
 | Vivelle 0.025 mg/day † (N=47) N (%) | Vivelle 0.0375 mg/day † (N=130) N (%) | Vivelle 0.05 mg/day † (N=103) N (%) | Vivelle 0.075 mg/day † (N=46) N (%) | Vivelle 0.1 mg/day † (N=132) 2 N (%) | Placebo (N=157) N (%)
Gastrointestinal disorders
Constipation | 2 (4.3) | 5 (3.8) | 4 (3.9) | 3 (6.5) | 2 (1.5) | 4 (2.5)
Dyspepsia | 4 (8.5) | 12 (9.2) | 3 (2.9) | 2 (4.3) | 0 | 10 (6.4)
Nausea | 2 (4.3) | 8 (6.2) | 4 (3.9) | 0 | 7 (5.3) | 5 (3.2)
General disorders and administration site conditions ***
Influenza-like illness | 3 (6.4) | 6 (4.6) | 8 (7.8) | 0 | 3 (2.3) | 10 (6.4)
Pain NOS* | 0 | 8 (6.2) | 0 | 2 (4.3) | 7 (5.3) | 7 (4.5)
Infections and infestations
Influenza | 4 (8.5) | 4 (3.1) | 6 (5.8) | 0 | 10 (7.6) | 14 (8.9)
Nasopharyngitis | 3 (6.4) | 16 (12.3) | 10 (9.7) | 9 (19.6) | 11 (8.3) | 24 (15.3)
Sinusitis NOS* | 4 (8.5) | 17 (13.1) | 13 (12.6) | 3 (6.5) | 7 (5.3) | 16 (10.2)
Upper respiratory tract infection NOS* | 3 (6.4) | 8 (6.2) | 11 (10.7) | 4 (8.7) | 6 (4.5) | 9 (5.7)
Investigations
Weight increased | 4 (8.5) | 5 (3.8) | 2 (1.9) | 2 (4.3) | 0 | 3 (1.9)
Musculoskeletal and connective tissue disorders
Arthralgia | 0 | 11 (8.5) | 4 (3.9) | 2 (4.3) | 5 (3.8) | 9 (5.7)
Back pain | 4 (8.5) | 10 (7.7) | 9 (8.7) | 4 (8.7) | 14 (10.6) | 10 (6.4)
Neck pain | 3 (6.4) | 4 (3.1) | 4 (3.9) | 0 | 6 (4.5) | 2 (1.3)
Pain in limb | 0 | 10 (7.7) | 7 (6.8) | 2 (4.3) | 6 (4.5) | 9 (5.7)
Nervous system disorders
Headache NOS* | 7 (14.9) | 35 (26.9) | 32 (31.1) | 23 (50.0) | 34 (25.8) | 37 (23.6)
Sinus headache | 0 | 12 (9.2) | 5 (4.9) | 5 (10.9) | 2 (1.5) | 8 (5.1)
Psychiatric disorders
Anxiety NEC ** | 3 (6.4) | 5 (3.8) | 0 | 0 | 2 (1.5) | 4 (2.5)
Depression | 5 (10.6) | 4 (3.1) | 7 (6.8) | 0 | 4 (3.0) | 6 (3.8)
Insomnia | 3 (6.4) | 6 (4.6) | 4 (3.9) | 2 (4.3) | 2 (1.5) | 9 (5.7)
Reproductive system and breast disorders
Breast tenderness | 8 (17.0) | 10 (7.7) | 8 (7.8) | 3 (6.5) | 17 (12.9) | 0
Dysmenorrhea | 0 | 0 | 0 | 3 (6.5) | 0 | 0
Intermenstrual bleeding | 3 (6.4) | 9 (6.9) | 6 (5.8) | 0 | 14 (10.6) | 7 (4.5)
Respiratory, thoracic and mediastinal disorders
Sinus congestion | 0 | 4 (3.1) | 3 (2.9) | 3 (6.5) | 6 (4.5) | 7 (4.5)
Vascular disorders
Hot flushes NOS* | 3 (6.4) | 0 | 3 (2.9) | 0 | 0 | 6 (3.8)
Hypertension NOS* | 2 (4.3) | 0 | 3 (2.9) | 0 | 0 | 2 (1.3)
† Represents milligrams of estradiol delivered daily by each system
*NOS represents not otherwise specified
**NEC represents not elsewhere classified
***Application site erythema and application site irritation were observed in 3.2% or less of patients across treatment groups.

During the clinical pharmacology studies with MINIVELLE, 35 percent or less of subjects experienced barely perceptible erythema. No transdermal systems were removed due to irritation. Three subjects (2.2 percent) reported mild discomfort while wearing MINIVELLE (N=136).

6.2 Postmarketing Experience

The following adverse reactions have been identified during post-approval use of MINIVELLE. Because these reactions are reported voluntarily from a population of uncertain size, it is not always possible to reliably estimate their frequency or establish a causal relationship to drug exposure.

Breast

Breast enlargement

Cardiovascular

Palpitations, angina unstable

Gastrointestinal

Hemorrhage, diarrhea

Skin

Application site reactions, erythema, rash, hyperhidrosis, pruritis, urticaria

Central Nervous System

Dizziness, paresthesia, migraine, mood swings, emotional disorder, irritability, nervousness

Miscellaneous

Portal vein thrombosis, dyspnea, malaise, fatigue, peripheral edema, muscle spasms, paresthesia oral, swollen tongue, lip swelling, pharyngeal edema

7 DRUG INTERACTIONS

In vitro and in vivo studies have shown that estrogens are metabolized partially by cytochrome P450 3A4 (CYP3A4). Therefore, inducers or inhibitors of CYP3A4 may affect estrogen drug metabolism. Inducers of CYP3A4 such as St. John’s wort (Hypericum perforatum) preparations, phenobarbital, carbamazepine and rifampin may reduce plasma concentrations of estrogens, possibly resulting in a decrease in therapeutic effects and/or changes in the uterine bleeding profile. Inhibitors of CYP3A4 such as erythromycin, clarithromycin, ketoconazole, itraconazole, ritonavir, and grapefruit juice may increase plasma concentrations of estrogens and may result in adverse reactions.

8 USE IN SPECIFIC POPULATIONS

8.1 Pregnancy

Risk Summary

MINIVELLE is not indicated for use in pregnancy. There are no data with the use of MINIVELLE in pregnant women; however, epidemiologic studies and meta-analyses have not found an increased risk of genital or nongenital birth defects (including cardiac anomalies and limb-reduction defects) following exposure to combined hormonal contraceptives (estrogens and progestins) before conception or during early pregnancy.

In the U.S. general population, the estimated background risk of major birth defects and miscarriage in clinically recognized pregnancies is 2% to 4% and 15% to 20%, respectively.

8.2 Lactation

Risk Summary

Estrogens are present in human milk and can reduce milk production in breast-feeding women. This reduction can occur at any time but is less likely to occur once breast-feeding is well established.

The developmental and health benefits of breastfeeding should be considered along with the mother’s clinical need for MINIVELLE and any potential adverse effects on the breastfed child from MINIVELLE or from the underlying maternal condition.

8.4 Pediatric Use

MINIVELLE is not indicated for use in pediatric patients. Clinical studies have not been conducted in the pediatric population.

8.5 Geriatric Use

There have not been sufficient numbers of geriatric women involved in clinical studies utilizing MINIVELLE to determine whether those over 65 years of age differ from younger subjects in their response to MINIVELLE.

The Women’s Health Initiative Studies

In the WHI estrogen-alone substudy (daily CE [0.625 mg]-alone versus placebo), there was a higher relative risk of stroke in women greater than 65 years of age [see Clinical Studies (14.3)].

In the WHI estrogen plus progestin substudy (daily CE [0.625 mg] plus MPA [2.5 mg] versus placebo), there was a higher relative risk of nonfatal stroke and invasive breast cancer in women greater than 65 years of age [see Warnings and Precautions (5.1), and Clinical Studies (14.3)].

The Women’s Health Initiative Memory Study

In the WHIMS ancillary studies of postmenopausal women 65 to 79 years of age, there was an increased risk of probable dementia in women receiving estrogen-alone or estrogen plus progestin when compared to placebo [see Warnings and Precautions (5.3), and Clinical Studies (14.4)].

Since both ancillary studies were conducted in women 65 to 79 years of age, it is unknown whether these findings apply to younger postmenopausal women^8 [see Warnings and Precautions (5.3), and Clinical Studies (14.3)] .

10 OVERDOSAGE

Overdosage of estrogen may cause nausea, vomiting, breast tenderness, abdominal pain, drowsiness and fatigue, and withdrawal bleeding may occur in women. Treatment of overdose consists of discontinuation of MINIVELLE therapy with institution of appropriate symptomatic care.

11 DESCRIPTION

MINIVELLE (estradiol transdermal system) contains estradiol in a multipolymeric adhesive. The system is designed to release estradiol continuously upon application to intact skin.

Five dosage strengths of MINIVELLE are available to provide nominal in vivo delivery rates of 0.025, 0.0375, 0.05, 0.075, or 0.1 mg of estradiol per day via the skin. Each corresponding system has an active surface area of 1.65, 2.48, 3.30, 4.95, or 6.6 cm^2 and contains 0.41, 0.62, 0.83, 1.24, or 1.65 mg of estradiol USP, respectively. The composition of the systems per unit area is identical.

Estradiol USP is a white, crystalline powder, chemically described as estra-1,3,5 (10)-triene-3,17β-diol.

The structural formula is

The molecular formula of estradiol is C18H2402. The molecular weight is 272.39

MINIVELLE is comprised of three layers. Proceeding from the visible surface toward the surface attached to the skin, these layers are (1) a polyolefin laminate backing (2) an adhesive formulation containing estradiol, acrylic adhesive, silicone adhesive, oleyl alcohol, NF, povidone, USP and dipropylene glycol, and (3) a polyester release liner which is attached to the adhesive surface and must be removed before the system can be used.

The active component of the system is estradiol. The remaining components of the system are pharmacologically inactive.

12 CLINICAL PHARMACOLOGY

12.1 Mechanism of Action

Endogenous estrogens are largely responsible for the development and maintenance of the female reproductive system and secondary sexual characteristics. Although circulating estrogens exist in a dynamic equilibrium of metabolic interconversions, estradiol is the principal intracellular human estrogen and is substantially more potent than its metabolites, estrone and estriol, at the receptor level.

The primary source of estrogen in normally cycling adult women is the ovarian follicle, which secretes 70 to 500 mcg of estradiol daily, depending on the phase of the menstrual cycle. After menopause, most endogenous estrogen is produced by conversion of androstenedione, secreted by the adrenal cortex, to estrone in the peripheral tissues. Thus, estrone and the sulfate conjugated form, estrone sulfate, are the most abundant circulating estrogens in postmenopausal women.

Estrogens act through binding to nuclear receptors in estrogen responsive tissues. To date, two estrogen receptors have been identified. These vary in proportion from tissue to tissue.

Circulating estrogens modulate the pituitary secretion of the gonadotropins, luteinizing hormone (LH) and follicle stimulating hormone (FSH) through a negative feedback mechanism. Estrogens act to reduce the elevated concentrations of these hormones seen in postmenopausal women.

12.2 Pharmacodynamics

Generally, a serum estrogen concentration does not predict an individual woman’s therapeutic response to MINIVELLE nor her risk for adverse outcomes. Likewise, exposure comparisons across different estrogen products to infer efficacy or safety for the individual woman may not be valid.

12.3 Pharmacokinetics

Absorption

In a single-dose, two way-crossover clinical study conducted in 96 healthy, non-smoking postmenopausal women under fed condition, MINIVELLE (0.1 mg per day) was bioequivalent to Vivelle (0.1 mg per day) based on estradiol exposure (AUC0-84) and estradiol peak concentration (Cmax) following a single-dose on the lower abdomen for 84 hours.

Estradiol pharmacokinetics were characterized in a separate open-label, single-center, randomized, single-dose, three-way crossover study conducted in 36 healthy, non-smoking postmenopausal women (aged 40 to 65 years). MINIVELLE transdermal systems delivering nominal estradiol of approximately 0.025 mg, 0.05 mg, and 0.1 mg per day were applied to the lower abdomen under fed state in a crossover fashion for 84 hours. The mean estradiol pharmacokinetics parameters are summarized in Table 2. AUC and Cmax are dose proportional from 0.025 mg to 0.1 mg per day.

Table 2: Mean (SD) Serum Pharmacokinetic Parameters of Baseline-Uncorrected Estradiol following a Single Dose of MINIVELLE (N=36)
Parameter | 0.1 mg/day | 0.05 mg/day | 0.025 mg/day
AUC 84 (pg·hr/mL) | 5875 (1857) | 3057 (980) | 1763 (600)
AUC 120 (pg·hr/mL) | 6252 (1938) | 3320 (1038) | 1979 (648)
C max (pg/mL) | 117 (39.3) | 56.6 (17.6) | 30.3 (11.1)
T max (hr) a | 24.0 (8-60) | 24.0 (8-60) | 36.0 (8-84)
a Median (minimum-maximum)

Figure 1 illustrates the mean baseline-uncorrected estradiol serum concentrations of MINIVELLE at three different strengths.

Figure 1: Mean Baseline-Uncorrected Estradiol Serum Concentration-Time Profiles Following a Single Dose of MINIVELLE 0.1 mg per day (Treatment A), 0.05 mg per day (Treatment B), and 0.025 mg per day (Treatment C) (N=36)

Distribution

The distribution of exogenous estrogens is similar to that of endogenous estrogens. Estrogens are widely distributed in the body and are generally found in higher concentrations in the sex hormone target organs. Estrogens circulate in the blood largely bound to sex hormone-binding globulin (SHBG) and albumin.

Metabolism

Exogenous estrogens are metabolized in the same manner as endogenous estrogens. Circulating estrogens exist in a dynamic equilibrium of metabolic interconversions. These transformations take place mainly in the liver. Estradiol is converted reversibly to estrone, and both can be converted to estriol, which is a major urinary metabolite. Estrogens also undergo enterohepatic recirculation via sulfate and glucuronide conjugation in the liver, biliary secretion of conjugates into the intestine, and hydrolysis in the intestine followed by reabsorption. In postmenopausal women a significant portion of the circulating estrogens exist as sulfate conjugates, especially estrone sulfate, which serves as a circulating reservoir for the formation of more active estrogens.

Excretion

Estradiol, estrone and estriol are excreted in the urine along with glucuronide and sulfate conjugates. The mean half-life values of estradiol calculated from treatment groups in the bioequivalence study and dose-proportionality study after dosing with MINIVELLE ranged from 6.2 to 7.9 hours. After removal of the transdermal systems, serum concentrations of estradiol and estrone returned to baseline concentrations within 24 hours.

Adhesion and Adhesive Residue

Based on combined data from bioequivalence and dose proportionality studies consisting of 208 MINIVELLE observations, approximately 98 percent of the observations had an adhesion score of 0 (i.e., the skin adhesion rate was greater than or equal to 90 percent) over the 84-hour wear period. One woman had a complete detachment during the wear period. Approximately 65 percent of the transdermal systems evaluated in these studies were with MINIVELLE 0.1 mg per day (6.6 cm ^2 active surface area).

After removal of MINIVELLE, women had either no adhesive residue (score of 0) or light adhesive residue (score of 1). No woman had medium adhesive residue. Of the 208 MINIVELLE observations, 54 percent had light adhesive residue and 46 percent had no adhesive residue.

13 NONCLINICAL TOXICOLOGY

13.1 Carcinogenesis, Mutagenesis, Impairment of Fertility

Long-term, continuous administration of natural and synthetic estrogens in certain animal species increases the frequency of carcinomas of the breast, uterus, cervix, vagina, testis, and liver.

14 CLINICAL STUDIES

14.1 Effects on Vasomotor Symptoms in Postmenopausal Women

There have been no efficacy and safety trials conducted with MINIVELLE. In a pharmacokinetic study, MINIVELLE was shown to be bioequivalent to Vivelle.

In two controlled clinical trials with Vivelle, in a total of 356 women, the 0.075 and 0.1 mg doses were superior to placebo in relieving vasomotor symptoms at Weeks 4, 8 and 12 of treatment. In these studies, the 0.0375 and 0.05 mg doses did not differ from placebo at Week 4, therefore, a third 12-week placebo-controlled study in 255 women was performed with Vivelle to establish the efficacy of the lowest dose of 0.0375 mg. The baseline mean daily number of hot flushes in these 255 women was 11.5. Results at Weeks 4, 8, and 12 of treatment are shown in Figure 2.

Figure 2: Mean (SD) change from baseline in mean daily number of hot flushes for
Vivelle 0.0375 mg versus Placebo in a 12 week trial.

The 0.0375 mg dose was superior to placebo in reducing both the frequency and severity of vasomotor symptoms at Weeks 4, 8 and 12 of treatment.

14.2 Effects on Bone Mineral Density in Postmenopausal Women

There have been no bone efficacy and safety trials conducted with MINIVELLE. In a pharmacokinetic study, MINIVELLE was shown to be bioequivalent to Vivelle.

Efficacy and safety of Vivelle in the prevention of postmenopausal osteoporosis have been studied in a 2-year double-blind, randomized, placebo-controlled, parallel group study. A total of 261 hysterectomized (161) and non-hysterectomized (100), surgically or naturally menopausal women (within 5 years of menopause), with no evidence of osteoporosis (lumbar spine bone mineral density within 2 standard deviations of average peak bone mass, i.e., ≥0.0827 g/cm^2) were enrolled in this study; 194 women were randomized to one of the four doses of Vivelle (0.1, 0.05, 0.0375, or 0.025 mg/day) and 67 women to placebo. Over 2 years, study systems were applied to the buttock or the abdomen twice a week. Non-hysterectomized women received oral medroxyprogesterone acetate (2.5 mg/day) throughout the study.

The study population comprised naturally (82 percent) or surgically (18 percent) menopausal, hysterectomized (61 percent) or non-hysterectomized (39 percent) women with a mean age of 52.0 years (range 27 to 62 years); the mean duration of menopause was 31.7 months (range 2 to 72 months). Two hundred thirty-two (89 percent) randomized women (173 on active drug, 59 on placebo) contributed data to the analysis of percent change from baseline in bone mineral density (BMD) of the AP lumbar spine, the primary efficacy variable. Women were given supplemental dietary calcium (100 mg elemental calcium/day) but no supplemental vitamin D. There was an increase in BMD of the AP lumbar spine in all Vivelle dose groups; in contrast to this, a decrease in AP lumbar spine BMD was observed in placebo patients. All Vivelle doses were significantly superior to placebo (p<0.05) at all time points with the exception of Vivelle 0.05 mg/day at 6 months. The highest dose of Vivelle was superior to the three lower doses. There were no statistically significant differences in pairwise comparisons among the three lower doses (See Figure 3).

Figure 3: Bone mineral density – AP Lumbar spine

Least squares means of percentage change from baseline

All randomized women with at least one post-baseline assessment available with last post-baseline observation carried forward

Analysis of percent change from baseline in femoral neck BMD, a secondary efficacy outcome variable, showed qualitatively similar results; all doses of Vivelle were significantly superior to placebo (p<0.05) at 24 months. The highest Vivelle dose was superior to placebo at all time points. A mixture of significant and non-significant results were obtained for the lower dose groups at earlier time points. The highest Vivelle dose was superior to the three lower doses, and there were no significant differences among the three lower doses at this skeletal site (see Figure 4).

Figure 4: Bone mineral density - Femoral neck

Least squares means of percentage change from baseline

All randomized women with at least one post-baseline assessment available with last post-baseline observation carried forward

14.3 Women's Health Initiative Studies

The WHI enrolled approximately 27,000 predominantly healthy postmenopausal women in two substudies to assess the risks and benefits of daily oral CE (0.625 mg)-alone or in combination with MPA (2.5 mg) compared to placebo in the prevention of certain chronic diseases. The primary endpoint was the incidence of CHD (defined as nonfatal MI, silent MI and CHD death), with invasive breast cancer as the primary adverse outcome. A “global index” included the earliest occurrence of CHD, invasive breast cancer, stroke, PE, endometrial cancer (only in the CE plus MPA substudy), colorectal cancer, hip fracture, or death due to other cause. These substudies did not evaluate the effects of CE-alone or CE plus MPA on menopausal symptoms.

WHI Estrogen-Alone Substudy

The WHI estrogen-alone substudy was stopped early because an increased risk of stroke was observed, and it was deemed that no further information would be obtained regarding the risks and benefits of estrogen-alone in predetermined primary endpoints.

Results of the estrogen-alone substudy, which included 10,739 women (average 63 years of age, range 50 to 79; 75.3 percent White, 15.1 percent Black, 6.1 percent Hispanic, 3.6 percent Other), after an average follow- up of 7.1 years are presented in Table 3.

Table 3: Relative and Absolute Risk Seen in the Estrogen Alone Substudy of WHI a
Event | Relative Risk CE vs. Placebo (95% nCI b) | CE n = 5,310 | Placebo n = 5,429
Event | Relative Risk CE vs. Placebo (95% nCI b) | Absolute Risk per 10,000 Women-Years
CHD events c Non-fatal MI c CHD death c | 0.95 (0.78–1.16) 0.91 (0.73–1.14) 1.01 (0.71–1.43) | 54 40 16 | 57 43 16
All Strokes c Ischemic strokec | 1.33 (1.15–1.68) 1.55 (1.19–2.01) | 45 38 | 33 25
Deep vein thrombosis c,d | 1.47 (1.06–2.06) | 23 | 15
Pulmonary embolism c | 1.37 (0.90–2.07) | 14 | 10
Invasive breast cancer c | 0.80 (0.62–1.04) | 28 | 34
Colorectal cancer e | 1.08 (0.75–1.55) | 17 | 16
Hip fracture c | 0.65 (0.45–0.94) | 12 | 19
Vertebral fractures c,d | 0.64 (0.44–0.93) | 11 | 18
Lower arm/wrist fractures c,d | 0.58 (0.47–0.72) | 35 | 59
Total fractures c,d | 0.71 (0.64–0.80) | 144 | 197
Death due to other causes e,f | 1.08 (0.88–1.32) | 53 | 50
Overall mortality c,d | 1.04 (0.88–1.22) | 79 | 75
Global Index g | 1.02 (0.92–1.13) | 206 | 201
a Adapted from numerous WHI publications. WHI publications can be viewed at www.nhlbi.nih.gov/whi.
b Nominal confidence intervals unadjusted for multiple looks and multiple comparisons.
c Results are based on centrally adjudicated data for an average follow-up of 7.1 years.
d Not included in “global index”.
e Results are based on an average follow-up of 6.8 years.
f All deaths, except from breast or colorectal cancer, definite or probable CHD, PE, or cerebrovascular disease.
g A subset of the events was combined in a “global index”, defined as the earliest occurrence of CHD events. invasive breast cancer, stroke, PE, endometrial cancer, colorectal cancer, hip fracture, or death due to other causes.

For those outcomes included in the WHI “global index” that reached statistical significance, the absolute excess risk per 10,000 women-years in the group treated with CE-alone was 12 more strokes, while the absolute risk reduction per 10,000 women-years was 7 fewer hip fractures. ⁹ The absolute excess risk of events included in the “global index” was a non-significant 5 events per 10,000 women-years. There was no difference between the groups in terms of all-cause mortality.

No overall difference for primary CHD events (nonfatal MI, silent MI and CHD death) and invasive breast cancer incidence in women receiving CE-alone compared to placebo was reported in final centrally adjudicated results from the estrogen-alone substudy, after an average follow-up of 7.1 years.

Centrally adjudicated results for stroke events from the estrogen-alone substudy, after an average follow-up of 7.1 years, reported no significant differences in distribution of stroke subtype or severity, including fatal strokes, in women receiving CE-alone compared to placebo. Estrogen-alone increased the risk for ischemic stroke, and this excess risk was present in all subgroups of women examined. ¹⁰

Timing of the initiation of estrogen-alone therapy relative to the start of menopause may affect the overall risk benefit profile. The WHI estrogen-alone substudy, stratified by age, showed in women 50 to 59 years of age a non-significant trend toward reduced risk for CHD [hazard ratio (HR) 0.63 (95 percent CI, 0.36-1.09)] and overall mortality [HR 0.71 (95 percent CI, 0.46-1.11)].

WHI Estrogen Plus Progestin Substudy

The WHI estrogen plus progestin substudy was stopped early. According to the predefined stopping rule, after an average follow-up of 5.6 years of treatment, the increased risk of invasive breast cancer and cardiovascular events exceeded the specified benefits included in the “global index”. The absolute excess risk of events included in the “global index” was 19 per 10,000 women-years.

For those outcomes included in the WHI “global index” that reached statistical significance after 5.6 years of follow-up, the absolute excess risks per 10,000 women-years in the group treated with CE plus MPA were 7 more CHD events, 8 more strokes, 10 more PEs, and 8 more invasive breast cancers, while the absolute risk reduction per 10,000 women-years were 6 fewer colorectal cancers and 5 fewer hip fractures.

Results of the CE plus MPA substudy, which included 16,608 women (average 63 years of age, range 50 to 79; 83.9 percent White, 6.8 percent Black, 5.4 percent Hispanic, 3.9 percent Other) are presented in Table 4. These results reflect centrally adjudicated data after an average follow-up of 5.6 years.

Table 4: Relative and Absolute Risk Seen in the Estrogen Plus Progestin Substudy of WHI at an Average of 5.6 Years a,b
Event | Relative Risk CE/MPA vs. Placebo (95% nCI c) | CE/MPA (n = 8,506) | Placebo (n = 8,102)
Event | Relative Risk CE/MPA vs. Placebo (95% nCI c) | Absolute Risk per 10,000 Women-Years
CHD events Non-fatal MI CHD death | 1.23 (0.99–1.53) 1.28 (1.00–1.63) 1.10 (0.70–1.75) | 41 31 8 | 34 25 8
All strokes Ischemic stroke | 1.31 (1.03–1.68) 1.44 (1.09–1.90) | 33 26 | 25 18
Deep vein thrombosis d | 1.95 (1.43–2.67) | 26 | 13
Pulmonary embolism | 2.13 (1.45–3.11) | 18 | 8
Invasive breast cancer e | 1.24 (1.01–1.54) | 41 | 33
Colorectal cancer | 0.61 (0.42–0.87) | 10 | 16
Endometrial cancer d | 0.81 (0.48–1.36) | 6 | 7
Cervical cancer d | 1.44 (0.47–4.42) | 2 | 1
Hip fracture | 0.67 (0.47–0.96) | 11 | 16
Vertebral fractures d | 0.65 (0.46–0.92) | 11 | 17
Lower arm/wrist fractures d | 0.71 (0.59–0.85) | 44 | 62
Total fractures d | 0.76 (0.69–0.83) | 152 | 199
Overall mortality f | 1.00 (0.83–1.19) | 52 | 52
Global Index g | 1.13 (1.02–1.25) | 184 | 165
a Adapted from numerous WHI publications. WHI publications can be viewed at www.nhlbi.nih.gov/whi.
b Results are based on centrally adjudicated data.
c Nominal confidence intervals unadjusted for multiple looks and multiple comparisons.
d Not included in “global index”.
e Includes metastatic and non-metastatic breast cancer, with the exception of in situ breast cancer.
f All deaths, except from breast or colorectal cancer, definite or probable CHD, PE, or cerebrovascular disease.
g A subset of the events was combined in a “global index”, defined as the earliest occurrence of CHD events, invasive breast cancer, stroke, pulmonary embolism, endometrial cancer, colorectal cancer, hip fracture, or death due to other causes.

Timing of the initiation of estrogen plus progestin therapy relative to the start of menopause may affect the overall risk benefit profile. The WHI estrogen plus progestin substudy stratified for age showed in women 50 to 59 years of age a non-significant trend toward reduced risk for overall mortality [HR 0.69 (95 percent CI, 0.44-1.07)].

14.4 Women's Health Initiative Memory Study

The WHIMS estrogen-alone ancillary study of WHI enrolled 2,947 predominantly healthy hysterectomized postmenopausal women 65 to 79 years of age (45 percent were 65 to 69 years of age, 36 percent were 70 to 74 years of age, and 19 percent were 75 years of age and older) to evaluate the effects of daily CE (0.625 mg)-alone on the incidence of probable dementia (primary outcome) compared to placebo.

After an average follow-up of 5.2 years, the relative risk of probable dementia for CE-alone versus placebo was 1.49 (95 percent CI, 0.83-2.66). The absolute risk of probable dementia for CE-alone versus placebo was 37 versus 25 cases per 10,000 women-years. Probable dementia as defined in this study included Alzheimer’s disease (AD), vascular dementia (VaD) and mixed type (having features of both AD and VaD). The most common classification of probable dementia in the treatment group and the placebo group was AD. Since the ancillary study was conducted in women 65 to 79 years of age, it is unknown whether these findings apply to younger postmenopausal women [see Warnings and Precautions (5.3) and Use in Specific Populations (8.5)].

The WHIMS estrogen plus progestin ancillary study enrolled 4,532 predominantly healthy postmenopausal women 65 years of age and older (47 percent were 65 to 69 years of age, 35 percent were 70 to 74 years of age, and 18 percent were 75 years of age and older) to evaluate the effects of daily CE (0.625 mg) plus MPA (2.5 mg) on the incidence of probable dementia (primary outcome) compared to placebo.

After an average follow-up of 4 years, the relative risk of probable dementia for CE plus MPA versus placebo was 2.05 (95 percent CI, 1.21- 3.48). The absolute risk of probable dementia for CE plus MPA versus placebo was 45 versus 22 per 10,000 women-years. Probable dementia as defined in this study included AD, VaD and mixed type (having features of both AD and VaD). The most common classification of probable dementia in the treatment group and the placebo group was AD. Since the ancillary study was conducted in women 65 to 79 years of age, it is unknown whether these findings apply to younger postmenopausal women [see Warnings and Precautions (5.3), and Use in Specific Populations (8.5)].

When data from the two populations were pooled as planned in the WHIMS protocol, the reported overall relative risk for probable dementia was 1.76 (95 percent CI, 1.19-2.60). Differences between groups became apparent in the first year of treatment. It is unknown whether these findings apply to younger postmenopausal women [see Warnings and Precautions (5.3), and Use in Specific Populations (8.5)].

15 REFERENCES

1. Rossouw JE, et al. Postmenopausal Hormone Therapy and Risk of Cardiovascular Disease by Age and Years Since Menopause. JAMA. 2007;297:1465-1477.
2. Hsia J, et al. Conjugated Equine Estrogens and Coronary Heart Disease. Arch Int Med. 2006;166:357–365.
3. Curb JD, et al. Venous Thrombosis and Conjugated Equine Estrogen in Women Without a Uterus. Arch Int Med. 2006; 166:772-780.
4. Cushman M, et al. Estrogen Plus Progestin and Risk of Venous Thrombosis. JAMA. 2004;292:1573-1580.
5. Stefanick ML, et al. Effects of Conjugated Equine Estrogens on Breast Cancer and Mammography Screening in Postmenopausal Women with Hysterectomy. JAMA. 2006;295:1647-1657.
6. Chlebowski RT, et al. Influence of Estrogen Plus Progestin on Breast Cancer and Mammography in Healthy Postmenopausal Women. JAMA. 2003;289:3234-3253.
7. Anderson GL, et al. Effects of Estrogen Plus Progestin on Gynecologic Cancers and Associated Diagnostic Procedures. JAMA. 2003;290:1739-1748.
8. Shumaker SA, et al. Conjugated Equine Estrogens and Incidence of Probable Dementia and Mild Cognitive Impairment in Postmenopausal Women. JAMA. 2004;291:2947-2958.
9. Jackson RD, et al. Effects of Conjugated Equine Estrogen on Risk of Fractures and BMD in Postmenopausal Women With Hysterectomy: Results From the Women's Health Initiative Randomized Trial. J Bone Miner Res. 2006;21:817-828.
10. Hendrix SL, et al. Effects of Conjugated Equine Estrogen on Stroke in the Women's Health Initiative. Circulation. 2006;113:2425-2434.

16 HOW SUPPLIED/STORAGE AND HANDLING

16.1 How Supplied

MINIVELLE (estradiol transdermal system), 0.025 mg per day - each 1.65 cm^2 system contains 0.41 mg of estradiol USP for nominal* delivery of 0.025 mg of estradiol per day.

Patient Calendar Pack of 8 Systems…………………………………..NDC 68968-6625-8

MINIVELLE (estradiol transdermal system), 0.0375 mg per day - each 2.48 cm^2 system contains 0.62 mg of estradiol USP for nominal* delivery of 0.0375 mg of estradiol per day.

Patient Calendar Pack of 8 Systems…………………………………..NDC 68968-6637-8

MINIVELLE (estradiol transdermal system), 0.05 mg per day - each 3.3 cm^2 system contains 0.83 mg of estradiol USP for nominal* delivery of 0.05 mg of estradiol per day.

Patient Calendar Pack of 8 Systems………………………………….NDC 68968-6650-8

MINIVELLE (estradiol transdermal system), 0.075 mg per day - each 4.95 cm^2 system contains 1.24 mg of estradiol USP for nominal* delivery of 0.075 mg of estradiol per day.

Patient Calendar Pack of 8 Systems………………………………….NDC 68968-6675-8

MINIVELLE (estradiol transdermal system), 0.1 mg per day - each 6.6 cm^2 system contains 1.65 mg of estradiol USP for nominal* delivery of 0.1 mg of estradiol per day.

Patient Calendar Pack of 8 Systems………………………………….NDC 68968-6610-8

*See Description

16.2 Storage and Handling

Store at 20°C to 25°C (68°F to 77°F); excursions permitted between 15°C and 30°C (59°F and 86°F) [see USP Controlled Room Temperature]

Do not store unpouched. Apply immediately upon removal from the protective pouch.

Used transdermal systems still contain active hormone. To discard, fold the sticky side of the transdermal system together, place it in a sturdy child-proof container, and place this container in the trash. Used transdermal systems should not be flushed in the toilet.

17 PATIENT COUNSELING INFORMATION

Advise women to read the FDA-approved patient labeling (Patient Information and Instructions for Use).

Vaginal Bleeding

Inform postmenopausal women to report unusual vaginal bleeding to their healthcare providers as soon as possible [see Warnings and Precautions (5.2)]

Possible Serious Adverse Reactions with Estrogen–Alone Therapy

Inform postmenopausal women of possible serious adverse reactions of estrogen-alone therapy including Cardiovascular Disorders, Malignant Neoplasms, and Probable Dementia [see Warning and Precautions (5.1, 5.2, 5.3)].

Possible Common Adverse Reactions with Estrogen–Alone Therapy

Inform postmenopausal women of less serious but common adverse reactions of estrogen-alone therapy such as headache, breast pain and tenderness, nausea and vomiting.

PATIENT INFORMATION

MINIVELLE (MIN-ee-vell)

(estradiol transdermal system)

Read this Patient Information before you start using MINIVELLE and each time you get a refill. There may be new information. This information does not take the place of talking to your healthcare provider about your menopausal symptoms or your treatment.

What is the most important information I should know about MINIVELLE (an estrogen hormone)?

- Using estrogen-alone may increase your chance of getting cancer of the uterus (womb).
- Report any unusual vaginal bleeding right away while you are using MINIVELLE. Vaginal bleeding after menopause may be a warning sign of cancer of the uterus (womb). Your healthcare provider should check any unusual vaginal bleeding to find out the cause.
- Do not use estrogen-alone to prevent heart disease, heart attacks, strokes, or dementia (decline in brain function).
- Using estrogen-alone may increase your chances of getting strokes or blood clots.
- Using estrogen-alone may increase your chance of getting dementia, based on a study of women 65 years of age and older.
- Do not use estrogens with progestogens to prevent heart disease, heart attacks, strokes, or dementia.
- Using estrogens with progestogens may increase your chances of getting heart attacks, strokes, breast cancer, or blood clots.
- Using estrogens with progestogens may increase your chance of getting dementia, based on a study of women 65 years of age and older.
- Only one estrogen-alone product and dose have been shown to increase your chances of getting strokes, blood clots, and dementia. Only one estrogen with progestogen product and dose have been shown to increase your chances of getting heart attacks, strokes, breast cancer, blood clots, and dementia.

Because other products and doses have not been studied in the same way, it is not known how the use of MINIVELLE will affect your chances of developing these conditions. You and your healthcare provider should talk regularly about whether you still need treatment with MINIVELLE.

What is MINIVELLE?

MINIVELLE is a prescription medicine patch (transdermal system) that contains the estrogen hormone estradiol. When applied to the skin, estradiol is absorbed through the skin into the bloodstream.

What is MINIVELLE® used for?

MINIVELLE is used after menopause to:

- Reduce moderate to severe hot flashes
  Estrogens are hormones made by a woman’s ovaries. The ovaries normally stop making estrogens when a woman is between 45 and 55 years old. This drop in body estrogen levels causes the “change of life” or menopause (the end of monthly menstrual periods). Sometimes, both ovaries are removed during an operation before natural menopause takes place. The sudden drop in estrogen levels causes “surgical menopause.”
  When estrogen levels begin dropping, some women develop very uncomfortable symptoms, such as feelings of warmth in the face, neck, and chest or sudden intense feelings of heat and sweating (“hot flashes” or “hot flushes”). In some women, the symptoms are mild and they will not need estrogens. In other women, symptoms can be more severe.
- Help reduce your chances of getting osteoporosis (thin weak bones)
  Osteoporosis from menopause is a thinning of the bones that makes them weaker and easier to break. If you use MINIVELLE only to prevent osteoporosis due to menopause, talk with your healthcare provider about whether a different treatment or medicine without estrogens might be better for you.
  You and your healthcare provider should talk regularly about whether you should continue treatment with MINIVELLE.

Who should not use MINIVELLE? Do not start using MINIVELLE if you:

- have unusual vaginal bleeding
  Vaginal bleeding after menopause may be a warning sign of cancer of the uterus (womb). Your healthcare provider should check any unusual vaginal bleeding to find out the cause.
- have been diagnosed with a bleeding disorder
- currently have or have had certain cancers
  Estrogens may increase the chances of getting certain types of cancers, including cancer of the breast or uterus (womb). If you have or have had cancer, talk with your healthcare provider about whether you should use MINIVELLE.
- had a stroke or heart attack
- currently have or have had blood clots
- currently have or have had liver problems
- are allergic to MINIVELLE or the ingredients in it. See the list of ingredients in MINIVELLE at the end of this leaflet.

Before you use MINIVELLE, tell your healthcare provider about all of your medical conditions, including if you:

- have any unusual vaginal bleeding
  Vaginal bleeding after menopause may be a warning sign of cancer of the uterus (womb). Your healthcare provider should check any unusual vaginal bleeding to find out the cause.
- have any other medical conditions that may become worse while you are using MINIVELLE
  Your healthcare provider may need to check you more carefully if you have certain conditions such as asthma (wheezing), diabetes, epilepsy (seizures), migraine, endometriosis, lupus, angioedema (swelling of the face and tongue), problems with your heart, liver, thyroid, kidneys, or have high calcium levels in your blood.
- are going to have surgery or will be on bed rest
  Your healthcare provider will let you know if you need to stop using MINIVELLE.
- are pregnant or think you may be pregnant.
  MINIVELLE is not for pregnant women.
- are breast feeding
  The hormone in MINIVELLE can pass into your breast milk.

Tell your healthcare provider about all the medicines you take, including prescription and over-the-counter medicines, vitamins and herbal supplements. Some medicines may affect how MINIVELLE works. MINIVELLE may also affect how your other medicines work. Keep a list of your medicines and show it to your healthcare provider and pharmacist when you get a new medicine.

How should I use MINIVELLE?

For detailed instructions, see the step-by-step instructions for using MINIVELLE at the end of this Patient Information

- Use MINIVELLE exactly as your healthcare provider tells you to use it
- MINIVELLE is for skin use only
- Change your MINIVELLE patch 2 times a week or every 3 to 4 days
- Apply your MINIVELLE patch to a clean, dry area on your lower abdomen or buttocks. This area must be clean, dry, and free of powder, oil or lotion for your patch to stick to your skin
- Apply your MINIVELLE patch to a different area of your abdomen or your buttocks each time. Do not use the same application site 2 times in the same week.
- Do not apply MINIVELLE to your breasts
- If you forget to apply a new MINIVELLE patch, apply a new patch as soon as possible.
- You and your healthcare provider should talk regularly (every 3 to 6 months) about your dose and whether you still need treatment with MINIVELLE.

How to Change MINIVELLE

- When changing the patch, peel off the used patch slowly from the skin.
- After removal of MINIVELLE if any adhesive residue remains on your skin, allow the area to dry for 15 minutes. Then, gently rub the area with oil or lotion to remove the adhesive from your skin
- Apply the new patch to a different area of your abdomen or buttocks. This area must be clean, dry, cool and free of powder, oil or lotion.

What are the possible side effects of MINIVELLE?

Side effects are grouped by how serious they are and how often they happen when you are treated.

Serious, but less common side effects include:

- heart attack
- stroke
- blood clots
- breast cancer
- cancer of the lining of the uterus (womb)
- cancer of the ovary
- dementia
- high or low blood calcium
- gallbladder disease
- visual abnormalities
- high blood pressure
- high levels of fat (triglyceride) in your blood
- liver problems
- changes in your thyroid hormone levels
- fluid retention
- cancer changes of endometriosis
- enlargement of benign tumors of the uterus (“fibroids”)
- worsening of swelling of face and tongue (angioedema) in women with a history of angioedema

Call your healthcare provider right away if you get any of the following warning signs or any other unusual symptoms that concern you:

- new breast lumps
- unusual vaginal bleeding
- changes in vision or speech
- sudden new severe headaches
- severe pains in your chest or legs with or without shortness of breath, weakness and fatigue
- swelling of face and tongue with or without red, itchy bumps

Common side effects of MINIVELLE include:

- headache
- breast pain
- irregular vaginal bleeding or spotting
- stomach or abdominal cramps, bloating
- nausea and vomiting
- hair loss
- fluid retention
- vaginal yeast infection
- redness and/or irritation at patch placement site

These are not all the possible side effects of MINIVELLE. For more information, ask your healthcare provider or pharmacist. Tell your healthcare provider if you have any side effects that bother you or do not go away. You may report side effects to Noven at 1-800-455-8070 or to FDA at 1-800-FDA-1088.

What can I do to lower my chances of a serious side effect with MINIVELLE?

- Talk with your healthcare provider regularly about whether you should continue using MINIVELLE.
- If you have a uterus, talk to your healthcare provider about whether the addition of a progestogen is right for you. In general, the addition of a progestogen is generally recommended for a woman with a uterus to reduce the chance of getting cancer of the uterus (womb).
- See your healthcare provider right away if you get vaginal bleeding while using MINIVELLE.
- Have a pelvic exam, breast exam and mammogram (breast X-ray) every year unless your healthcare provider tells you something else. If members of your family have had breast cancer or if you have ever had breast lumps or an abnormal mammogram, you may need to have breast exams more often.
- If you have high blood pressure, high cholesterol (fat in the blood), diabetes, are overweight, or if you use tobacco, you may have higher chances of getting heart disease. Ask your healthcare provider for ways to lower your chances of getting heart disease.

How should I store and throw away used MINIVELLE patches?

- Store MINIVELLE at room temperature 68°F to 77°F (20°C to 25°C)
- Do not store MINIVELLE patches outside of their pouches. Apply immediately upon removal from the protective pouch
- Used patches still contain estrogen. To throw away the patch, fold the sticky side of the patch together, place it in a sturdy child-proof container, and place this container in the trash. Used patches should not be flushed in the toilet

KEEP MINIVELLE and all other medicines out of the reach of children

General information about safe and effective use of MINIVELLE

Medicines are sometimes prescribed for purposes other than those listed in Patient Information leaflets. Do not use MINIVELLE for conditions for which it was not prescribed. Do not give MINIVELLE to other people, even if they have the same symptoms you have. It may harm them.

You can ask your healthcare provider or pharmacist for information about MINIVELLE that is written for health professionals. You can get more information by calling Noven Pharmaceuticals, Inc. at 1-800-455-8070.

What are the ingredients in MINIVELLE?

Active ingredient: estradiol

Inactive ingredients: Polyolefin laminate backing, acrylic and silicone adhesives, oleyl alcohol, NF, povidone, USP and dipropylene glycol and a polyester release liner

INSTRUCTIONS FOR USE

MINIVELLE® (MIN-ee-vell)

(estradiol transdermal system)

Read this PATIENT INFORMATION before you start using MINIVELLE and each time you get a refill. There may be new information. This information does not take the place of talking to your healthcare provider about your menopausal symptoms or your treatment.

You will need the following supplies (See Figure A).

Figure A

Step 1: Pick the days you will change your patch.

- You will need to change your patch 2 times a week or every 3 to 4 days. Use the calendar printed inside your carton to choose the 2 days you will change your patch (See Figure B).
- Remember to change your patch on the same 2 days you marked on your calendar. If you forget to change your patch on the correct date, apply a new patch as soon as you remember, and continue to follow your original schedule

Figure B

Step 2. Remove the MINIVELLE patch from the pouch.

- Remove the patch from its protective pouch by tearing at the notch (do not use scissors, See Figure C).
- Do not remove your patch from the protective pouch until you are ready to apply it

Figure C

Step 3. Remove half of the adhesive liner (See Figure D).

Figure D

Step 4. Placing the patch on your skin.

- Hold the part of the patch that still has the adhesive liner on it
- Avoid touching the sticky half of the patch with your fingers
- Apply the exposed sticky half of the patch to 1 of the areas of skin shown below (See Figures E and F).

Note:

- Avoid the waistline, since clothing and belts may cause the patch to be rubbed off
- Do not apply the patch to your breasts
- Only apply the patch to skin that is clean, dry, and free of any powder, oil, or lotion
- You should not apply the patch to injured, burned, or irritated skin, or areas with skin conditions (such as birth marks, tattoos, or that is very hairy)

Step 5: Press the patch firmly onto your skin.

- Remove the remaining half of the adhesive liner and press the entire patch into place with the palm of your hand for 10 seconds
- Rub the edges of the patch with your fingers to make sure that it will stick to your skin (See Figure G).

Figure G

Note:

- Showering will not cause your patch to fall off
- If your patch falls off reapply it. If you cannot reapply the patch, apply a new patch to another area (See Figures E and D) and continue to follow your original placement schedule
- If you stop using your MINIVELLE patch or forget to apply a new patch as scheduled, you may have spotting, or bleeding, and recurrence of symptoms

Step 6: Throwing away your used patch.

- When it is time to change your patch, remove the old patch before you apply a new patch
- To throw away the patch, fold the sticky side of the patch together, place it in a sturdy child-proof container, and place this container in the trash. Used patches should not be flushed in the toilet

This Patient Information and Instructions for Use have been approved by the U.S. Food and Drug Administration.

Manufactured by:
Noven Pharmaceuticals Inc.
Miami, FL 33186

Approved (02/2024)

Package Label - Principal Display Panel – 0.025mg Trade Carton

NDC 68968-6625-8

0.025 mg/day

Minivelle®

(estradiol transdermal system)

Delivers 0.025 mg/day

Twice-Weekly

Rx Only

Includes 8 Systems

Open Here

Contents: 8 Systems

Rx Only

Each 1.65 cm^2 system contains 0.41 mg of estradiol USP.

Inactive components: acrylic adhesive, silicone adhesive, oleyl alcohol, dipropylene glycol, povidone, polyolefin laminate backing, polyester release liner.

For Transdermal Use Only

Important: Package not child-resistant.

Apply immediate upon removal from pouch.

Do not store unpouched.

Store at 20°C to 25°C (68°F to 77°F).

[See USP Controlled Room Temperature].

Dosage and Administration: Apply twice-weekly. See package insert.

N3 68968-6625-8 7

302348-3

Noven

Your application schedule

Determine which 2 days of the week you will change your patch and then mark them on this calender

º Sunday/Wednesday º Thursday/Sunday

º Monday/Thursday º Friday/Monday

º Tuesday/Friday º Saturday/Tuesday

º Wednesday/Saturday

As a handy reminder of your application schedule, keep this tear out with you

Pull here for your Minivelle® patches

0.025 mg/day

Mfd. by: Noven Pharmaceuticals, Inc.

Miami, Florida 33186

Dist. by: Noven Therapeutics, LLC

Miami, Florida 33186

0.025 mg/day

Minivelle®

(estradiol transdermal system)

Delivers 0.025 mg/day

01440

30248-3

LOT/EXP

GTIN: 00368968662587

Package Label - Principal Display Panel – 0.0375mg Carton

NDC 68968-6637-8

0.0375 mg/day

Minivelle®

(estradiol transdermal system)

Delivers 0.0375 mg/day

Twice-Weekly

Rx Only

Includes 8 Systems

Open Here

Contents: 8 Systems

Rx Only

Each 2.48 cm^2 system contains 0.62 mg of estradiol USP.

Inactive components: acrylic adhesive, silicone adhesive, oleyl alcohol, dipropylene glycol, povidone, polyolefin laminate backing, polyester release liner.

For Transdermal Use Only

Important: Package not child-resistant.

Apply immediate upon removal from pouch.

Do not store unpouched.

Store at 20°C to 25°C (68°F to 77°F).

[See USP Controlled Room Temperature].

Dosage and Administration: Apply twice-weekly. See package insert.

N3 68968-6637-8 2

302360-4

Noven

Your application schedule

Determine which 2 days of the week you will change your patch and then mark them on this calender

º Sunday/Wednesday º Thursday/Sunday

º Monday/Thursday º Friday/Monday

º Tuesday/Friday º Saturday/Tuesday

º Wednesday/Saturday

As a handy reminder of your application schedule, keep this tear out with you

Pull here for your Minivelle® patches

0.0375 mg/day

Mfd. by: Noven Pharmaceuticals, Inc.

Miami, Florida 33186

Dist. by: Noven Therapeutics, LLC

Miami, Florida 33186

0.0375 mg/day

Minivelle®

(estradiol transdermal system)

Delivers 0.025 mg/day

01440

30248-3

LOT/EXP

GTIN: 00368968663782

Package Label - Principal Display Panel – 0.05mg Carton

NDC 68968-6650-8

0.05 mg/day

Minivelle®

(estradiol transdermal system)

Delivers 0.05 mg/day

Twice-Weekly

Rx Only

Includes 8 Systems

Open Here

Contents: 8 Systems

Rx Only

Each 3.3 cm^2 system contains 1.83 mg of estradiol USP.

Inactive components: acrylic adhesive, silicone adhesive, oleyl alcohol, dipropylene glycol, povidone, polyolefin laminate backing, polyester release liner.

For Transdermal Use Only

Important: Package not child-resistant.

Apply immediate upon removal from pouch.

Do not store unpouched.

Store at 20°C to 25°C (68°F to 77°F).

[See USP Controlled Room Temperature].

Dosage and Administration: Apply twice-weekly. See package insert.

N3 68968-6650-8 3

302360-4

Noven

Your application schedule

Determine which 2 days of the week you will change your patch and then mark them on this calender

º Sunday/Wednesday º Thursday/Sunday

º Monday/Thursday º Friday/Monday

º Tuesday/Friday º Saturday/Tuesday

º Wednesday/Saturday

As a handy reminder of your application schedule, keep this tear out with you

Pull here for your Minivelle® patches

0.05 mg/day

Mfd. by: Noven Pharmaceuticals, Inc.

Miami, Florida 33186

Dist. by: Noven Therapeutics, LLC

Miami, Florida 33186

0.05 mg/day

Minivelle®

(estradiol transdermal system)

Delivers 0.025 mg/day

01440

30248-3

LOT/EXP

GTIN: 00368968665083

Package Label - Principal Display Panel – 0.075mg Carton

NDC 68968-6675-8

0.075 mg/day

Minivelle®

(estradiol transdermal system)

Delivers 0.05 mg/day

Twice-Weekly

Rx Only

Includes 8 Systems

Open Here

Contents: 8 Systems

Rx Only

Each 4.95 cm^2 system contains 1.24 mg of estradiol USP.

Inactive components: acrylic adhesive, silicone adhesive, oleyl alcohol, dipropylene glycol, povidone, polyolefin laminate backing, polyester release liner.

For Transdermal Use Only

Important: Package not child-resistant.

Apply immediate upon removal from pouch.

Do not store unpouched.

Store at 20°C to 25°C (68°F to 77°F).

[See USP Controlled Room Temperature].

Dosage and Administration: Apply twice-weekly. See package insert.

N3 68968-6675-8 2

302360-4

Noven

Your application schedule

Determine which 2 days of the week you will change your patch and then mark them on this calender

º Sunday/Wednesday º Thursday/Sunday

º Monday/Thursday º Friday/Monday

º Tuesday/Friday º Saturday/Tuesday

º Wednesday/Saturday

As a handy reminder of your application schedule, keep this tear out with you

Pull here for your Minivelle® patches

0.075 mg/day

Mfd. by: Noven Pharmaceuticals, Inc.

Miami, Florida 33186

Dist. by: Noven Therapeutics, LLC

Miami, Florida 33186

0.05 mg/day

Minivelle®

(estradiol transdermal system)

Delivers 0.025 mg/day

01440

302357-3

LOT/EXP

GTIN: 003689686637582

Package Label - Principal Display Panel – 0.1mg Carton

NDC 68968-6610-8

0.1 mg/day

Minivelle®

(estradiol transdermal system)

Delivers 0.05 mg/day

Twice-Weekly

Rx Only

Includes 8 Systems

Open Here

Contents: 8 Systems

Rx Only

Each 6.6 cm^2 system contains 1.65 mg of estradiol USP.

Inactive components: acrylic adhesive, silicone adhesive, oleyl alcohol, dipropylene glycol, povidone, polyolefin laminate backing, polyester release liner.

For Transdermal Use Only

Important: Package not child-resistant.

Apply immediate upon removal from pouch.

Do not store unpouched.

Store at 20°C to 25°C (68°F to 77°F).

[See USP Controlled Room Temperature].

Dosage and Administration: Apply twice-weekly. See package insert.

N3 68968-6610-8 5

302360-4

Noven

Your application schedule

Determine which 2 days of the week you will change your patch and then mark them on this calender

º Sunday/Wednesday º Thursday/Sunday

º Monday/Thursday º Friday/Monday

º Tuesday/Friday º Saturday/Tuesday

º Wednesday/Saturday

As a handy reminder of your application schedule, keep this tear out with you

Pull here for your Minivelle® patches

0.1 mg/day

Mfd. by: Noven Pharmaceuticals, Inc.

Miami, Florida 33186

Dist. by: Noven Therapeutics, LLC

Miami, Florida 33186

0.1 mg/day

Minivelle®

(estradiol transdermal system)

Delivers 0.025 mg/day

01440

302351-4

LOT/EXP

GTIN: 00368968661085